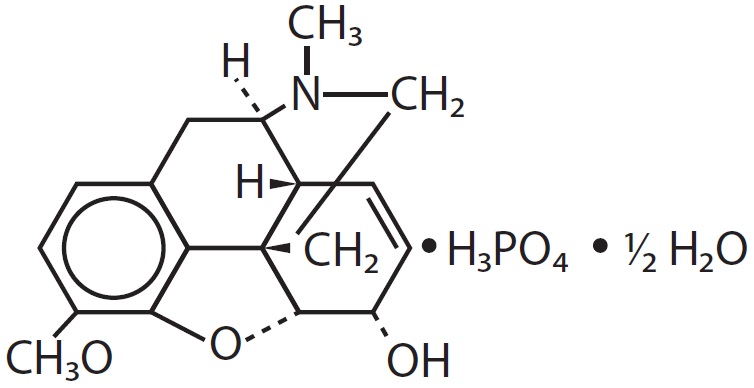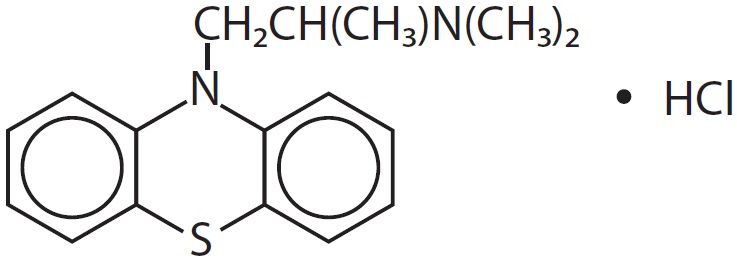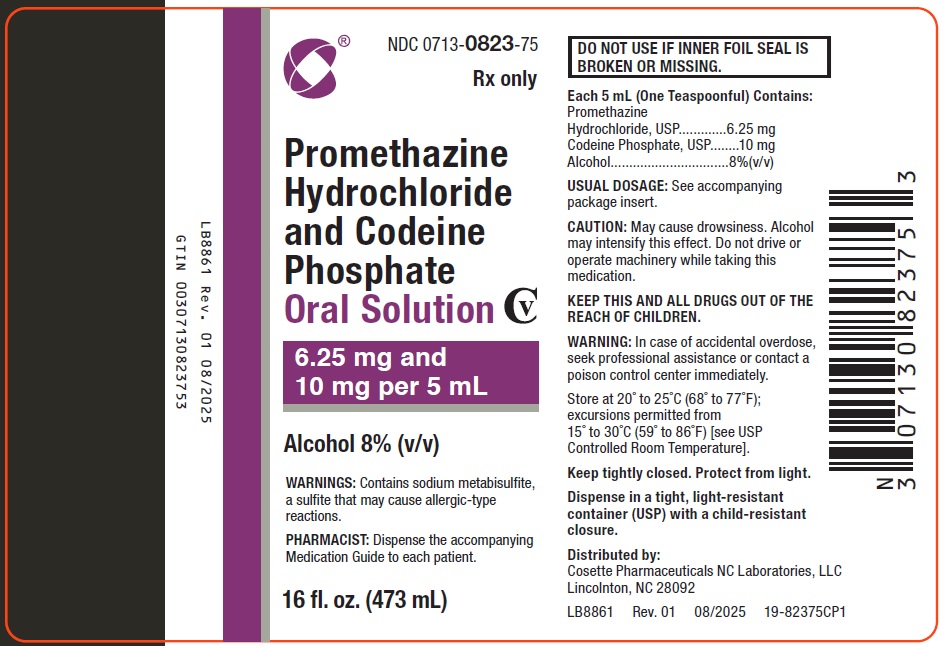 DRUG LABEL: Promethazine Hydrochloride and Codeine Phosphate
NDC: 0713-0823 | Form: SOLUTION
Manufacturer: Cosette Pharmaceuticals, Inc.
Category: prescription | Type: HUMAN PRESCRIPTION DRUG LABEL
Date: 20251218
DEA Schedule: CV

ACTIVE INGREDIENTS: PROMETHAZINE HYDROCHLORIDE 6.25 mg/5 mL; CODEINE PHOSPHATE 10 mg/5 mL
INACTIVE INGREDIENTS: ANHYDROUS CITRIC ACID; ASCORBIC ACID; D&C RED NO. 33; EDETATE DISODIUM; ALCOHOL; FD&C BLUE NO. 1; METHYLPARABEN; MINT; PEACH; PROPYLENE GLYCOL; PROPYLPARABEN; SACCHARIN SODIUM; SODIUM BENZOATE; SODIUM CITRATE; SODIUM METABISULFITE; SUCROSE; WATER

HIGHLIGHTS OF PRESCRIBING INFORMATION

These highlights do not include all the information needed to use PROMETHAZINE HCL AND CODEINE PHOSPHATE ORAL SOLUTION safely and effectively. See full prescribing information for PROMETHAZINE HCL AND CODEINE PHOSPHATE ORAL SOLUTION.
PROMETHAZINE HCL and CODEINE PHOSPHATE oral solution, CV
Initial U.S. Approval: 1952

WARNING: ADDICTION, ABUSE, AND MISUSE; LIFE-THREATENING RESPIRATORY DEPRESSION; ACCIDENTAL INGESTION; ULTRA-RAPID METABOLISM OF CODEINE AND OTHER RISK FACTORS FOR LIFE-THREATENING RESPIRATORY DEPRESSION IN CHILDREN; PROMETHAZINE AND RESPIRATORY DEPRESSION IN CHILDREN; MEDICATION ERRORS; INTERACTIONS WITH DRUGS AFFECTING CYTOCHROME P450 ISOENZYMES; CONCOMITANT USE WITH BENZODIAZEPINES OR OTHER CNS DEPRESSANTS; NEONATAL OPIOID WITHDRAWAL SYNDROME

See full prescribing information for complete boxed warning.

- Promethazine HCl and Codeine Phosphate Oral Solution exposes users to risks of addiction, abuse, and misuse, which can lead to overdose and death. Assess patient’s risk before prescribing and monitor closely for these behaviors and conditions. (5.1)
- Serious, life-threatening, or fatal respiratory depression may occur. Monitor closely, especially upon initiation or when used in patients at higher risk. (5.2)
- Accidental ingestion of Promethazine HCl and Codeine Phosphate Oral Solution, especially by children, can result in a fatal overdose of codeine. (5.2)
- Life-threatening respiratory depression and death have occurred in children who received codeine; most cases followed tonsillectomy and/or adenoidectomy, and many of the children had evidence of being an ultra-rapid metabolizer of codeine due to a CYP2D6 polymorphism. (5.3) Promethazine HCl and Codeine Phosphate Oral Solution is contraindicated in children younger than 12 years of age and in children younger than 18 years of age following tonsillectomy and/or adenoidectomy. (4) Avoid the use of Promethazine HCl and Codeine Phosphate Oral Solution in adolescents 12 to 18 years of age who have other risk factors that may increase their sensitivity to the respiratory depressant effects of codeine.
- Postmarketing cases of respiratory depression, including fatalities have been reported with use of promethazine in pediatric patients. Children may be particularly sensitive to the additive respiratory depressant effects when promethazine is combined with other respiratory depressants, including codeine. (5.4)
- Ensure accuracy when prescribing, dispensing, and administering Promethazine HCl and Codeine Phosphate Oral Solution. Dosing errors can result in accidental overdose and death. (2.1, 5.7)
- The effects of concomitant use or discontinuation of cytochrome P450 3A4 inducers, 3A4 inhibitors, or 2D6 inhibitors with codeine are complex, requiring careful consideration of the effects on the parent drug, codeine, and the active metabolite, morphine. Avoid the use of Promethazine HCl and Codeine Phosphate Oral Solution in patients who are taking a CYP3A4 inhibitor, CYP3A4 inducer, or 2D6 inhibitor. (5.9, 7.1, 7.2, 7.3)
- Concomitant use of opioids with benzodiazepines or other central nervous system (CNS) depressants, including alcohol, may result in profound sedation, respiratory depression, coma, and death. Avoid the use of Promethazine HCl and Codeine Phosphate Oral Solution in patients taking benzodiazepines, other CNS depressants, or alcohol. (5.10, 7.4)
- Promethazine HCl and Codeine Phosphate Oral Solution is not recommended for use in pregnant women. Prolonged use of Promethazine HCl and Codeine Phosphate Oral Solution during pregnancy can result in neonatal opioid withdrawal syndrome, which may be life-threatening if not recognized and treated. If Promethazine HCl and Codeine Phosphate Oral Solution is used for a prolonged period in a pregnant woman, advise the patient of the risk of neonatal opioid withdrawal syndrome and ensure that appropriate treatment will be available. (5.19, 8.1)

1 INDICATIONS AND USAGE

Promethazine HCl and Codeine Phosphate Oral Solution is a combination of codeine, an opioid agonist; and promethazine, a phenothiazine, indicated for the temporary relief of cough and upper respiratory symptoms associated with allergy or the common cold in patients 18 years of age and older. (1)

Important Limitations of Use (1)

- Not indicated for pediatric patients under 18 years of age.
- Because of the risks of addiction, abuse, and misuse with opioids, even at recommended doses, reserve Promethazine HCl and Codeine Phosphate Oral Solution for use in adult patients for whom the benefits of cough suppression are expected to outweigh the risks, and in whom an adequate assessment of the etiology of the cough has been made.

2 DOSAGE AND ADMINISTRATION

- Adults 18 years of age and older: 5 mL every 4 to 6 hours as needed, not to exceed 6 doses (30 mL) in 24 hours. (2.2)
- Measure Promethazine HCl and Codeine Phosphate Oral Solution with an accurate milliliter measuring device. (2.1, 5.7)
- Do not increase the dose or dosing frequency. (2.1)
- Prescribe for the shortest duration consistent with treatment goals. (2.3)
- Reevaluate patients with unresponsive cough in 5 days or sooner for possible underlying pathology. (2.3)
- Reevaluate patient prior to refilling. (2.3)

3 DOSAGE FORMS AND STRENGTHS

Oral solution: Each 5 mL contains codeine phosphate, 10 mg and promethazine hydrochloride 6.25 mg, in a clear, purple red, peach-mint flavor syrup. (3)

4 CONTRAINDICATIONS

- Children younger than 12 years of age. (4)
- Significant respiratory depression. (4)
- Acute or severe bronchial asthma in an unmonitored setting or in absence of resuscitative equipment. (4)
- Known or suspected gastrointestinal obstruction, including paralytic ileus. (4)
- Concurrent use of monoamine oxidase inhibitor (MAOI) therapy or within the last 14 days. (4)
- History of an idiosyncratic reaction to promethazine or to other phenothiazines. (4)
- Hypersensitivity to codeine or other opiates, promethazine, or any of the inactive ingredients in Promethazine HCl and Codeine Phosphate Oral Solution. (4)

5 WARNINGS AND PRECAUTIONS

See Boxed WARNINGS

- Life-threatening respiratory depression in patients with chronic pulmonary disease or in elderly, cachectic, or debilitated patients: Monitor closely, particularly during initiation of therapy. (5.6)
- Activities requiring mental alertness: Avoid engaging in hazardous tasks requiring mental alertness such as driving or operating machinery. (5.8)
- Risks of use in patients with head injury, impaired consciousness, increased intracranial pressure, or brain tumors: Avoid use. May increase intracranial pressure and obscure the clinical course of head injuries. (5.12)
- Neuroleptic Malignant Syndrome: Monitor during therapy. (5.13)
- Paradoxical Reactions: Monitor during therapy. (5.14)
- Seizures in patients with seizure disorders: Monitor during therapy. (5.15)
- Bone marrow depression: Use with caution in patients with bone marrow depression. (5.17)
- Severe hypotension: Monitor during initiation of therapy. Avoid use in patients with circulatory shock. (5.18)
- Adrenal insufficiency: If diagnosed, treat with physiologic replacement of corticosteroids, and wean patient off of the opioid. (5.20)

6 ADVERSE REACTIONS

Common adverse reactions include: Sedation (somnolence, mental clouding, lethargy), impaired mental and physical performance, lightheadedness, dizziness, headache, dry mouth, nausea, vomiting, constipation, shortness of breath, and sweating. (6)

To report SUSPECTED ADVERSE REACTIONS, contact Cosette Pharmaceuticals, Inc. at 1-800-922-1038 or FDA at 1-800-FDA-1088 or www.fda.gov/medwatch.

7 DRUG INTERACTIONS

- Serotonergic Drugs: Concomitant use may result in serotonin syndrome. Discontinue if serotonin syndrome is suspected. (7.5)
- Muscle relaxants: Avoid concomitant use. (7.7)
- Diuretics: Codeine may reduce the efficacy of diuretics. Monitor for reduced effect. (7.8)
- Anticholinergic drugs: Concurrent use may cause paralytic ileus. (5.11, 7.9)

8 USE IN SPECIFIC POPULATIONS

- Pregnancy: Avoid use in pregnant women. May cause fetal harm. (8.1)
- Lactation: Breastfeeding not recommended. (8.2)
- Renal Impairment: Use with caution in patients with severe renal impairment. (8.6)
- Hepatic Impairment: Use with caution in patients with severe hepatic impairment. (8.7)

FULL PRESCRIBING INFORMATION

WARNING: ADDICTION, ABUSE, AND MISUSE; LIFE-THREATENING RESPIRATORY DEPRESSION; ACCIDENTAL INGESTION; ULTRA-RAPID METABOLISM OF CODEINE AND OTHER RISK FACTORS FOR LIFE-THREATENING RESPIRATORY DEPRESSION IN CHILDREN; PROMETHAZINE AND RESPIRATORY DEPRESSION IN CHILDREN; MEDICATION ERRORS; INTERACTIONS WITH DRUGS AFFECTING CYTOCHROME P450 ISOENZYMES; CONCOMITANT USE WITH BENZODIAZEPINES OR OTHER CNS DEPRESSANTS; NEONATAL OPIOID WITHDRAWAL SYNDROME

Addiction, Abuse, and Misuse
Promethazine HCl and Codeine Phosphate Oral Solution exposes patients and other users to the risks of opioid addiction, abuse, and misuse, which can lead to overdose and death. Reserve Promethazine HCl and Codeine Phosphate Oral Solution for use in adult patients for whom the benefits of cough suppression are expected to outweigh the risks, and in whom an adequate assessment of the etiology of the cough has been made. Assess each patient’s risk prior to prescribing Promethazine HCl and Codeine Phosphate Oral Solution, prescribe Promethazine HCl and Codeine Phosphate Oral Solution for the shortest duration that is consistent with individual patient treatment goals, monitor all patients regularly for the development of addiction or abuse, and refill only after reevaluation of the need for continued treatment. [see Warnings and Precautions (5.1)].

Life-Threatening Respiratory Depression
Serious, life-threatening, or fatal respiratory depression may occur with use of Promethazine HCl and Codeine Phosphate Oral Solution. Monitor for respiratory depression, especially during initiation of Promethazine HCl and Codeine Phosphate Oral Solution therapy or when used in patients at higher risk [see Warnings and Precautions (5.2)].

Accidental Ingestion
Accidental ingestion of even one dose of Promethazine HCl and Codeine Phosphate Oral Solution, especially by children, can result in a fatal overdose of codeine [see Warnings and Precautions (5.2)].

Ultra-Rapid Metabolism of Codeine and Other Risk Factors for Life-Threatening Respiratory Depression in Children

Life-threatening respiratory depression and death have occurred in children who received codeine. Most of the reported cases occurred following tonsillectomy and/or adenoidectomy, and many of the children had evidence of being an ultra-rapid metabolizer of codeine due to a CYP2D6 polymorphism [see Warnings and Precautions (5.3)]. Promethazine HCl and Codeine Phosphate Oral Solution is contraindicated in children younger than 12 years of age and in children younger than 18 years of age following tonsillectomy and/or adenoidectomy [see Contraindications (4)]. Avoid the use of Promethazine HCl and Codeine Phosphate Oral Solution in adolescents 12 to 18 years of age who have other risk factors that may increase their sensitivity to the respiratory depressant effects of codeine.

Promethazine and Respiratory Depression in Children
Postmarketing cases of respiratory depression, including fatalities have been reported with use of promethazine in pediatric patients. Children may be particularly sensitive to the additive respiratory depressant effects when promethazine is combined with other respiratory depressants, including codeine [see Warnings and Precautions (5.4)].

Risk of Medication Errors
Ensure accuracy when prescribing, dispensing, and administering Promethazine HCl and Codeine Phosphate Oral Solution. Dosing errors can result in accidental overdose and death. Always use an accurate milliliter measuring device when measuring and administering Promethazine HCl and Codeine Phosphate Oral Solution [see Dosage and Administration (2.1), Warnings and Precautions (5.7)].

Interactions with Drugs Affecting Cytochrome P450 Isoenzymes
The effects of concomitant use or discontinuation of cytochrome P450 3A4 inducers, 3A4 inhibitors, or 2D6 inhibitors with codeine are complex, requiring careful consideration of the effects on the parent drug, codeine, and the active metabolite, morphine. Avoid the use of Promethazine HCl and Codeine Phosphate Oral Solution in patients who are taking a CYP3A4 inhibitor, CYP3A4 inducer, or 2D6 inhibitor [see Warnings and Precautions (5.9), Drug Interactions (7.1, 7.2, 7.3)].

Risks from Concomitant Use with Benzodiazepines or Other CNS Depressants

Concomitant use of opioids with benzodiazepines or other central nervous system (CNS) depressants, including alcohol, may result in profound sedation, respiratory depression, coma, and death. Avoid the use of Promethazine HCl and Codeine Phosphate Oral Solution in patients taking benzodiazepines, other CNS depressants, or alcohol [see Warnings and Precautions (5.10), Drug Interactions (7.4)].

Neonatal Opioid Withdrawal Syndrome
Promethazine HCl and Codeine Phosphate Oral Solution is not recommended for use in pregnant women [see Use in Specific Populations (8.1)]. Prolonged use of Promethazine HCl and Codeine Phosphate Oral Solution during pregnancy can result in neonatal opioid withdrawal syndrome, which may be life-threatening if not recognized and treated, and requires management according to protocols developed by neonatology experts. If Promethazine HCl and Codeine Phosphate Oral Solution is used for a prolonged period in a pregnant woman, advise the patient of the risk of neonatal opioid withdrawal syndrome and ensure that appropriate treatment will be available [see Warnings and Precautions (5.20)].

1 INDICATIONS AND USAGE

Promethazine HCl and Codeine Phosphate Oral Solution is indicated for the temporary relief of coughs and upper respiratory symptoms associated with allergy or the common cold in patients 18 years of age and older.

Important Limitations of Use

- Not indicated for pediatric patients under 18 years of age [see Use in Specific Populations (8.4)].
- Contraindicated in pediatric patients under 12 years of age [see Contraindications (4), Use in Specific Populations (8.4)].
- Contraindicated in pediatric patients 12 to 18 years of age after tonsillectomy or adenoidectomy [see Contraindications (4), Use in Specific Populations (8.4)].
- Because of the risks of addiction, abuse, and misuse with opioids, even at recommended doses [see Warnings and Precautions (5.1)], reserve Promethazine HCl and Codeine Phosphate Oral Solution for use in adult patients for whom the benefits of cough suppression are expected to outweigh the risks, and in whom an adequate assessment of the etiology of the cough has been made.

2 DOSAGE AND ADMINISTRATION

2.1 Important Dosage and Administration Instructions

Administer Promethazine HCl and Codeine Phosphate Oral Solution by the oral route only.

Always use an accurate milliliter measuring device when administering Promethazine HCl and Codeine Phosphate Oral Solution to ensure that the dose is measured and administered accurately. A household teaspoon is not an accurate measuring device and could lead to overdosage [see Warnings and Precautions (5.7)]. For prescriptions where a measuring device is not provided, a pharmacist can provide an appropriate measuring device and can provide instructions for measuring the correct dose. Do not overfill. Rinse the measuring device with water after each use.

Advise patients not to increase the dose or dosing frequency of Promethazine HCl and Codeine Phosphate Oral Solution because serious adverse events such as respiratory depression may occur with overdosage [see Warnings and Precautions (5.1), Overdosage (10)]. The dosage of Promethazine HCl and Codeine Phosphate Oral Solution should not be increased if cough fails to respond; an unresponsive cough should be reevaluated for possible underlying pathology [see Dosage and Administration (2.3), Warnings and Precautions (5.6)].

2.2 Recommended Dosage

Adults 18 years of age and older: 5 mL every 4 to 6 hours as needed, not to exceed 6 doses (30 mL) in 24 hours.

2.3 Monitoring, Maintenance, and Discontinuation of Therapy

Prescribe Promethazine HCl and Codeine Phosphate Oral Solution for the shortest duration that is consistent with individual patient treatment goals [see Warnings and Precautions (5.1)].

Monitor patients closely for respiratory depression, especially within the first 24-72 hours of initiating therapy [see Warnings and Precautions (5.2)].

Reevaluate patients with unresponsive cough in 5 days or sooner for possible underlying pathology, such as foreign body or lower respiratory tract disease [see Warnings and Precautions (5.6)]. If a patient requires a refill, reevaluate the cause of the cough and assess the need for continued treatment with Promethazine HCl and Codeine Phosphate Oral Solution, the relative incidence of adverse reactions, and the development of addiction, abuse, or misuse [see Warnings and Precautions (5.1)].

Do not abruptly discontinue Promethazine HCl and Codeine Phosphate Oral Solution in a physically-dependent patient [see Drug Abuse and Dependence (9.3)]. When a patient who has been taking Promethazine HCl and Codeine Phosphate Oral Solution regularly and may be physically dependent no longer requires therapy with Promethazine HCl and Codeine Phosphate Oral Solution, taper the dose gradually, by 25% to 50% every 2 to 4 days, while monitoring carefully for signs and symptoms of withdrawal. If the patient develops these signs or symptoms, raise the dose to the previous level and taper more slowly, either by increasing the interval between decreases, decreasing the amount of change in dose, or both.

3 DOSAGE FORMS AND STRENGTHS

Oral solution: Each 5 mL contains codeine phosphate, 10 mg and promethazine hydrochloride 6.25 mg, in a flavored syrup base [see Description (11)].

4 CONTRAINDICATIONS

Promethazine HCl and Codeine Phosphate Oral Solution is contraindicated for:

- All children younger than 12 years of age [see Warnings and Precautions (5.2, 5.3, 5.5), Use in Specific Populations (8.4)].
- Postoperative pain management in children younger than 18 years of age following tonsillectomy and/or adenoidectomy [see Warnings and Precautions (5.2, 5.3)].

Promethazine HCl and Codeine Phosphate Oral Solution is also contraindicated in patients with:

- Significant respiratory depression [see Warnings and Precautions (5.2)].
- Acute or severe bronchial asthma in an unmonitored setting or in the absence of resuscitative equipment [see Warnings and Precautions (5.6)].
- Known or suspected gastrointestinal obstruction, including paralytic ileus [see Warnings and Precautions (5.11)].
- A history of an idiosyncratic reaction to promethazine or to other phenothiazines [see Warnings and Precautions (5.14)].
- Concurrent use of monoamine oxidase inhibitors (MAOIs) or use of MAOIs within 14 days [see Warnings and Precautions (5.16), Drug Interactions (7.6)].
- Hypersensitivity to codeine, promethazine, or any of the inactive ingredients in Promethazine HCl and Codeine Phosphate Oral Solution [see Adverse Reactions (6)]. Persons known to be hypersensitive to certain other opioids may exhibit cross-reactivity to codeine.

5 WARNINGS AND PRECAUTIONS

5.1 Addiction, Abuse, and Misuse

Promethazine HCl and Codeine Phosphate Oral Solution contains codeine, a Schedule V controlled substance. As an opioid, Promethazine HCl and Codeine Phosphate Oral Solution exposes users to the risks of addiction, abuse, and misuse [see Drug Abuse and Dependence (9)], which can lead to overdose and death [see Overdosage (10)]. Reserve Promethazine HCl and Codeine Phosphate Oral Solution for use in adult patients for whom the benefits of cough suppression are expected to outweigh the risks, and in whom an adequate assessment of the etiology of the cough has been made. Assess each patient’s risk prior to prescribing Promethazine HCl and Codeine Phosphate Oral Solution, prescribe Promethazine HCl and Codeine Phosphate Oral Solution for the shortest duration that is consistent with individual patient treatment goals, monitor all patients regularly for the development of addiction or abuse, and refill only after reevaluation of the need for continued treatment.

Although the risk of addiction in any individual is unknown, it can occur in patients appropriately prescribed Promethazine HCl and Codeine Phosphate Oral Solution. Addiction can occur at recommended dosages and if the drug is misused or abused. Risks are increased in patients with a personal or family history of substance abuse (including drug or alcohol abuse or addiction) or mental illness (e.g., major depression). Opioids are sought by drug abusers and people with addiction disorders and are subject to criminal diversion. Consider these risks when prescribing or dispensing Promethazine HCl and Codeine Phosphate Oral Solution. Strategies to reduce these risks include prescribing the drug in the smallest appropriate quantity and advising the patient on the proper disposal of unused drug [see Patient Counseling Information (17)]. Contact local state professional licensing board or state controlled substances authority for information on how to prevent and detect abuse or diversion of this product.

5.2 Life-Threatening Respiratory Depression

Serious, life-threatening, or fatal respiratory depression has been reported with the use of opioids, including codeine, one of the active ingredients in Promethazine HCl and Codeine Phosphate Oral Solution. Codeine produces dose-related respiratory depression by directly acting on the brain stem respiratory center that controls respiratory rhythm and may produce irregular and periodic breathing. Codeine is subject to variability in metabolism based upon CYP2D6 genotype, which can lead to an increased exposure to the active metabolite morphine [see Warnings and Precautions (5.3)]. Promethazine exerts a depressant effect on the respiratory center that is independent of and additive to that of other respiratory depressants, including codeine [see Warnings and Precautions (5.4)]. Respiratory depression, if not immediately recognized and treated, may lead to respiratory arrest and death. Management of respiratory depression includes discontinuation of Promethazine HCl and Codeine Phosphate Oral Solution, close observation, supportive measures, and use of opioid antagonists (e.g. naloxone), depending on the patient’s clinical status [see Overdosage (10)]. Carbon dioxide (CO2) retention from opioid-induced respiratory depression can exacerbate the sedating effects of opioids.

While serious, life-threatening, or fatal respiratory depression can occur at any time during the use of Promethazine HCl and Codeine Phosphate Oral Solution, the risk is greatest during the initiation of therapy, when Promethazine HCl and Codeine Phosphate Oral Solution is used concomitantly with other drugs that may cause respiratory depression [see Warnings and Precautions (5.10)], in patients with chronic pulmonary disease or decreased respiratory reserve, and in patients with altered pharmacokinetics or altered clearance (e.g. elderly, cachectic, or debilitated patients) [see Warnings and Precautions (5.6)].

To reduce the risk of respiratory depression, proper dosing of Promethazine HCl and Codeine Phosphate Oral Solution is essential [see Dosage and Administration (2.1), Warnings and Precautions (5.7)]. Monitor patients closely, especially within the first 24-72 hours of initiating therapy or when used in patients at higher risk.

Overdose of codeine in adults has been associated with fatal respiratory depression, and the use of codeine in children younger than 12 years of age has been associated with fatal respiratory depression when used as recommended [see Warnings and Precautions (5.3)]. Accidental ingestion of even one dose of Promethazine HCl and Codeine Phosphate Oral Solution, especially by children, can result in respiratory depression and death.

5.3 Ultra-Rapid Metabolism of Codeine and Other Risk Factors for Life-Threatening Respiratory Depression in Children

Life-threatening respiratory depression and death have occurred in children who received codeine. Codeine is subject to variability in metabolism based upon CYP2D6 genotype (described below), which can lead to an increased exposure to the active metabolite morphine. Based upon post-marketing reports, children younger than 12 years old appear to be more susceptible to the respiratory depressant effects of codeine, particularly if there are risk factors for respiratory depression. For example, many reported cases of death occurred in the post-operative period following tonsillectomy and/or adenoidectomy, and many of the children had evidence of being ultra-rapid metabolizers of codeine. Furthermore, children with obstructive sleep apnea who are treated with codeine for post-tonsillectomy and/or adenoidectomy pain may be particularly sensitive to its respiratory depressant effect. Because of the risk of life-threatening respiratory depression and death:

- Promethazine HCl and Codeine Phosphate Oral Solution is contraindicated in all children younger than 12 years of age [see Contraindications (4)].
- Promethazine HCl and Codeine Phosphate Oral Solution is contraindicated for post-operative management in pediatric patients younger than 18 years of age following tonsillectomy and/or adenoidectomy [see Contraindications (4)].
- Avoid the use of Promethazine HCl and Codeine Phosphate Oral Solution in adolescents 12 to 18 years of age who have other risk factors that may increase their sensitivity to the respiratory depressant effects of codeine. Risk factors include conditions associated with hypoventilation, such as postoperative status, obstructive sleep apnea, obesity, severe pulmonary disease, neuromuscular disease, and concomitant use of other medications that cause respiratory depression [see Warnings and Precautions (5.10), Use in Specific Populations (8.4)].
- Healthcare providers should choose the lowest effective dose for the shortest period of time and inform patients and caregivers about these risks and the signs of morphine overdose [see Warnings and Precautions (5.1), Overdosage (10)].

Lactation

At least one death was reported in a nursing infant who was exposed to high levels of morphine in breast milk because the mother was an ultra-rapid metabolizer of codeine. Breastfeeding is not recommended during treatment with Promethazine HCl and Codeine Phosphate Oral Solution [see Use in Specific Populations (8.2)].

CYP2D6 Genetic Variability: Ultra-Rapid Metabolizers

Some individuals may be ultra-rapid metabolizers because of a specific CYP2D6 genotype (e.g., gene duplications denoted as *1/*1xN or *1/*2xN). The prevalence of this CYP2D6 phenotype varies widely and has been estimated at 1 to 10% for Whites (European, North American), 3 to 4% for Blacks (African Americans), 1 to 2% for East Asians (Chinese, Japanese, Korean), and may be greater than 10% in certain ethnic groups (i.e., Oceanian, Northern African, Middle Eastern, Ashkenazi Jews, Puerto Rican). These individuals convert codeine into its active metabolite, morphine, more rapidly and completely than other people. This rapid conversion results in higher than expected serum morphine levels. Even at labeled dosage regimens, individuals who are ultra-rapid metabolizers may have life-threatening or fatal respiratory depression or experience signs of overdose (such as extreme sleepiness, confusion, or shallow breathing) [see Overdosage (10)]. Therefore, individuals who are ultra-rapid metabolizers should not use Promethazine HCl and Codeine Phosphate Oral Solution.

5.4 Promethazine and Respiratory Depression

Children

Postmarketing cases of respiratory depression, including fatalities, have been reported with use of promethazine in pediatric patients. Concomitant administration with other respiratory depressants may increase the risk of respiratory depression. Children may be particularly sensitive to the additive respiratory depressant effects when promethazine is combined with other respiratory depressants, including codeine [see Warnings and Precautions (5.3, 5.5, 5.10)].

Excessively large dosages of antihistamines, including promethazine hydrochloride, in pediatric patients may cause sudden death [see Overdosage (10)].

Concomitant Conditions and Other Risk Factors

Avoid use of promethazine in patients at risk for respiratory depression. Risk factors include conditions associated with hypoventilation, such as postoperative status, obstructive sleep apnea, obesity, severe pulmonary disease, neuromuscular disease, and concomitant use of other medications that cause respiratory depression [see Warnings and Precautions (5.6, 5.10)].

5.5 Risks with Use in Pediatric Populations

Children are particularly sensitive to the respiratory depressant effects of codeine [see Warnings and Precautions (5.2, 5.3)] and promethazine [see Warnings and Precautions (5.4)]. Because of the risk of life-threatening respiratory depression and death, Promethazine HCl and Codeine Phosphate Oral Solution is contraindicated in children less than 12 years of age, and in pediatric patients younger than 18 years of age following tonsillectomy and/or adenoidectomy [see Contraindications (4)].

Use of Promethazine HCl and Codeine Phosphate Oral Solution in children also exposes them to the risks of addiction, abuse, and misuse [see Drug Abuse and Dependence (9)], which can lead to overdose and death [see Warnings and Precautions (5.1), Overdosage (10)]. Because the benefits of symptomatic treatment of cough associated with allergies or the common cold do not outweigh the risks of use of codeine in pediatric patients, Promethazine HCl and Codeine Phosphate Oral Solution is not indicated for use in patients younger than 18 years of age [see Indications (1), Use in Specific Populations (8.4)].

5.6 Risks with Use in Other At-Risk Populations

Unresponsive Cough

The dosage of Promethazine HCl and Codeine Phosphate Oral Solution should not be increased if cough fails to respond; an unresponsive cough should be reevaluated in 5 days or sooner for possible underlying pathology, such as foreign body or lower respiratory tract disease [see Dosage and Administration (2.3)].

Asthma and Other Pulmonary Disease

The use of Promethazine HCl and Codeine Phosphate Oral Solution in patients with acute or severe bronchial asthma in an unmonitored setting or in the absence of resuscitative equipment is contraindicated [see Contraindications (4)].

Opioid analgesics and antitussives, including codeine, one of the active ingredients in Promethazine HCl and Codeine Phosphate Oral Solution, should not be used in patients with acute febrile illness associated with productive cough or in patients with chronic respiratory disease where interference with ability to clear the tracheobronchial tree of secretions would have a deleterious effect on the patient’s respiratory function.

Promethazine HCl and Codeine Phosphate Oral Solution-treated patients with significant chronic obstructive pulmonary disease or cor pulmonale, and those with a substantially decreased respiratory reserve, hypoxia, hypercapnia, or pre-existing respiratory depression are at increased risk of decreased respiratory drive including apnea, even at recommended dosages of Promethazine HCl and Codeine Phosphate Oral Solution [see Warnings and Precautions (5.2)].

Elderly, Cachectic, or Debilitated Patients: Life-threatening respiratory depression is more likely to occur in elderly, cachectic, or debilitated patients because they may have altered pharmacokinetics or altered clearance compared to younger, healthier patients [see Warnings and Precautions (5.2)].

Because of the risk of respiratory depression, avoid the use of opioid antitussives, including Promethazine HCl and Codeine Phosphate Oral Solution in patients with compromised respiratory function, patients at risk of respiratory failure, and in elderly, cachectic, or debilitated patients. If Promethazine HCl and Codeine Phosphate Oral Solution is prescribed, monitor such patients closely, particularly when initiating Promethazine HCl and Codeine Phosphate Oral Solution and when Promethazine HCl and Codeine Phosphate Oral Solution is given concomitantly with other drugs that depress respiration [see Warnings and Precautions (5.10)].

5.7 Risk of Accidental Overdose and Death due to Medication Errors

Dosing errors can result in accidental overdose and death. To reduce the risk of overdose and respiratory depression, ensure that the dose of Promethazine HCl and Codeine Phosphate Oral Solution is communicated clearly and dispensed accurately [see Dosage and Administration (2.1)].

Advise patients to always use an accurate milliliter measuring device when measuring and administering Promethazine HCl and Codeine Phosphate Oral Solution. Inform patients that a household teaspoon is not an accurate measuring device and such use could lead to overdosage and serious adverse reactions [see Overdosage (10)]. For prescriptions where a measuring device is not provided, a pharmacist can provide an appropriate calibrated measuring device and can provide instructions for measuring the correct dose.

5.8 Activities Requiring Mental Alertness: Risks of Driving and Operating Machinery

Codeine and promethazine, two of the active ingredients in Promethazine HCl and Codeine Phosphate Oral Solution, may produce marked drowsiness and impair the mental and/or physical abilities required for the performance of potentially hazardous tasks such as driving a car or operating machinery. Advise patients to avoid engaging in hazardous tasks requiring mental alertness and motor coordination after ingestion of Promethazine HCl and Codeine Phosphate Oral Solution. Avoid concurrent use of Promethazine HCl and Codeine Phosphate Oral Solution with alcohol or other central nervous system depressants because additional impairment of central nervous system performance may occur [see Warnings and Precautions (5.10)].

5.9 Risks of Interactions with Drugs Affecting Cytochrome P450 Isoenzymes

The effects of concomitant use or discontinuation of cytochrome P450 3A4 inducers, 3A4 inhibitors, or 2D6 inhibitors with codeine are complex. Use of cytochrome P450 3A4 inducers, 3A4 inhibitors, or 2D6 inhibitors with Promethazine HCl and Codeine Phosphate Oral Solution requires careful consideration of the effects on the parent drug, codeine, and the active metabolite, morphine.

Cytochrome P450 3A4 Interaction

The concomitant use of Promethazine HCl and Codeine Phosphate Oral Solution with all cytochrome P450 3A4 inhibitors, such as macrolide antibiotics (e.g., erythromycin), azole-antifungal agents (e.g., ketoconazole), and protease inhibitors (e.g., ritonavir) or discontinuation of a cytochrome P450 3A4 inducer such as rifampin, carbamazepine, and phenytoin, may result in an increase in codeine plasma concentrations with subsequently greater metabolism by cytochrome P450 2D6, resulting in greater morphine levels, which could increase or prolong adverse reactions and may cause potentially fatal respiratory depression.

The concomitant use of Promethazine HCl and Codeine Phosphate Oral Solution with all cytochrome P450 3A4 inducers or discontinuation of a cytochrome P450 3A4 inhibitor may result in lower codeine levels, greater norcodeine levels, and less metabolism via 2D6 with resultant lower morphine levels. This may be associated with a decrease in efficacy, and in some patients, may result in signs and symptoms of opioid withdrawal.

Avoid the use of Promethazine HCl and Codeine Phosphate Oral Solution in patients who are taking a CYP3A4 inhibitor or CYP3A4 inducer. If concomitant use of Promethazine HCl and Codeine Phosphate Oral Solution with inhibitors and inducers of CYP3A4 is necessary, monitor patients for signs and symptoms that may reflect opioid toxicity and opioid withdrawal [see Drug Interactions (7.1, 7.2)].

Risks of Concomitant Use or Discontinuation of Cytochrome P450 2D6 Inhibitors

The concomitant use of Promethazine HCl and Codeine Phosphate Oral Solution with all cytochrome P450 2D6 inhibitors (e.g., amiodarone, quinidine) may result in an increase in codeine plasma concentrations and a decrease in active metabolite morphine plasma concentration which could result in an analgesic efficacy reduction or symptoms of opioid withdrawal.

Discontinuation of a concomitantly used cytochrome P450 2D6 inhibitor may result in a decrease in codeine plasma concentration and an increase in active metabolite morphine plasma concentration which could increase or prolong adverse reactions and may cause potentially fatal respiratory depression.

Avoid the use of Promethazine HCl and Codeine Phosphate Oral Solution in patients who are taking a CYP2D6 inhibitor. If concomitant use of Promethazine HCl and Codeine Phosphate Oral Solution with inhibitors of CYP2D6 is necessary, monitor patients for signs and symptoms that may reflect opioid toxicity and opioid withdrawal [see Drug Interactions (7.3)].

5.10 Risks from Concomitant Use with Benzodiazepines or other CNS Depressants

Concomitant use of opioids, including Promethazine HCl and Codeine Phosphate Oral Solution, with benzodiazepines, or other CNS depressants, including alcohol, may result in profound sedation, respiratory depression, coma, and death. Because of these risks, avoid use of opioid cough medications in patients taking benzodiazepines, other CNS depressants, or alcohol [see Drug Interactions (7.4)].

Observational studies have demonstrated that concomitant use of opioid analgesics and benzodiazepines increases the risk of drug-related mortality compared to use of opioids alone. Because of similar pharmacologic properties, it is reasonable to expect similar risk with concomitant use of opioid cough medications and benzodiazepines, other CNS depressants, or alcohol.

Advise both patients and caregivers about the risks of respiratory depression and sedation if Promethazine HCl and Codeine Phosphate Oral Solution is used with benzodiazepines, alcohol, or other CNS depressants [see Patient Counseling Information (17)].

5.11 Risks of Use in Patients with Gastrointestinal Conditions

Promethazine HCl and Codeine Phosphate Oral Solution is contraindicated in patients with known or suspected gastrointestinal obstruction, including paralytic ileus [see Contraindications (4)]. The use of codeine in Promethazine HCl and Codeine Phosphate Oral Solution may obscure the diagnosis or clinical course of patients with acute abdominal conditions.

The concurrent use of anticholinergics with Promethazine HCl and Codeine Phosphate Oral Solution may produce paralytic ileus [see Drug Interactions (7.9)].

The codeine in Promethazine HCl and Codeine Phosphate Oral Solution may result in constipation or obstructive bowel disease, especially in patients with underlying intestinal motility disorders. Use with caution in patients with underlying intestinal motility disorders.

The codeine in Promethazine HCl and Codeine Phosphate Oral Solution may cause spasm of the sphincter of Oddi, resulting in an increase in biliary tract pressure. Opioids may cause increases in serum amylase [see Warnings and Precautions (5.21)]. Monitor patients with biliary tract disease, including acute pancreatitis for worsening symptoms.

Administration of promethazine has been associated with reported cholestatic jaundice.

5.12 Risks of Use in Patients with Head Injury, Impaired Consciousness, Increased Intracranial Pressure, or Brain Tumors

Avoid the use of Promethazine HCl and Codeine Phosphate Oral Solution in patients with head injury, intracranial lesions, or a pre-existing increase in intracranial pressure. In patients who may be susceptible to the intracranial effects of CO2 retention (e.g., those with evidence of increased intracranial pressure or brain tumors), Promethazine HCl and Codeine Phosphate Oral Solution may reduce respiratory drive, and the resultant CO2 retention can further increase intracranial pressure. Furthermore, opioids produce adverse reactions that may obscure the clinical course of patients with head injuries.

5.13 Risk of Neuroleptic Malignant Syndrome

A potentially fatal symptom complex sometimes referred to as Neuroleptic Malignant Syndrome (NMS) has been reported in association with promethazine HCl alone or in combination with antipsychotic drugs. Clinical manifestations of NMS are hyperpyrexia, muscle rigidity, altered mental status and evidence of autonomic instability (irregular pulse or blood pressure, tachycardia, diaphoresis and cardiac dysrhythmias).

The diagnostic evaluation of patients with this syndrome is complicated. In arriving at a diagnosis, it is important to identify cases where the clinical presentation includes both serious medical illness (e.g., pneumonia, systemic infection, etc.) and untreated or inadequately treated extrapyramidal signs and symptoms (EPS). Other important considerations in the differential diagnosis include central anticholinergic toxicity, heat stroke, drug fever and primary central nervous system (CNS) pathology.

The management of NMS should include 1) immediate discontinuation of promethazine HCl, antipsychotic drugs, if any, and other drugs not essential to concurrent therapy, 2) intensive symptomatic treatment and medical monitoring, and 3) treatment of any concomitant serious medical problems for which specific treatments are available. There is no general agreement about specific pharmacological treatment regimens for uncomplicated NMS.

Since recurrences of NMS have been reported with phenothiazines, avoid use of Promethazine HCl and Codeine Phosphate Oral Solution in patients with a history consistent with NMS.

5.14 Risk of Paradoxical Reactions, including Dystonias

Promethazine HCl and Codeine Phosphate Oral Solution contains promethazine, a phenothiazine. Phenothiazines are associated with dystonic reactions, particularly in pediatric patients who have an acute illness associated with dehydration. Paradoxical reactions, including dystonia, torticollis, tongue protrusion, hyperexcitability, and abnormal movements have been reported in patients following a single administration of promethazine. Discontinue Promethazine HCl and Codeine Phosphate Oral Solution if a paradoxical reaction occurs.

5.15 Increased Risk of Seizures in Patients with Seizure Disorders

The codeine and promethazine in Promethazine HCl and Codeine Phosphate Oral Solution may increase the frequency of seizures in patients with seizure disorders, and may increase the risk of seizures occurring in other clinical settings associated with seizures. Monitor patients with a history of seizure disorders for worsened seizure control during Promethazine HCl and Codeine Phosphate Oral Solution therapy.

5.16 Co-administration with Monoamine Oxidase Inhibitors (MAOIs)

Concurrent use of Promethazine HCl and Codeine Phosphate Oral Solution is contraindicated in patients receiving monoamine oxidase inhibitors (MAOIs) or within 14 days of stopping such therapy [see Contraindications (4)]. MAOIs may potentiate the effects of morphine, codeine’s active metabolite, including respiratory depression, coma, and confusion MAOIs [see Drug Interactions (7.6)].

5.17 Bone-Marrow Depression

Promethazine HCl and Codeine Phosphate Oral Solution should be used with caution in patients with bonemarrow depression. Leukopenia and agranulocytosis have been reported, usually when promethazine has been used in association with other known marrow-toxic agents.

5.18 Severe Hypotension

Promethazine HCl and Codeine Phosphate Oral Solution may cause severe hypotension including orthostatic hypotension and syncope in ambulatory patients. There is increased risk in patients whose ability to maintain blood pressure has already been compromised by a reduced blood volume or concurrent administration of certain CNS depressant drugs (e.g., phenothiazines or general anesthetics) [see Drug Interactions (7.4)]. Monitor these patients for signs of hypotension after initiating Promethazine HCl and Codeine Phosphate Oral Solution.

In patients with circulatory shock, Promethazine HCl and Codeine Phosphate Oral Solution may cause vasodilation that can further reduce cardiac output and blood pressure. Avoid the use of Promethazine HCl and Codeine Phosphate Oral Solution in patients with circulatory shock.

5.19 Neonatal Opioid Withdrawal Syndrome

Promethazine HCl and Codeine Phosphate Oral Solution is not recommended for use in pregnant women. Prolonged use of Promethazine HCl and Codeine Phosphate Oral Solution during pregnancy can result in withdrawal in the neonate. Neonatal opioid withdrawal syndrome, unlike opioid withdrawal syndrome in adults, may be life-threatening if not recognized and treated, and requires management according to protocols developed by neonatology experts. Observe newborns for signs of neonatal opioid withdrawal syndrome and manage accordingly. Advise pregnant women using opioids for a prolonged period of the risk of neonatal opioid withdrawal syndrome and ensure that appropriate treatment will be available [see Use in Specific Populations (8.1), Patient Counseling Information (17)].

5.20 Adrenal Insufficiency

Cases of adrenal insufficiency have been reported with opioid use, more often following greater than one month of use. Presentation of adrenal insufficiency may include non-specific symptoms and signs including nausea, vomiting, anorexia, fatigue, weakness, dizziness, and low blood pressure. If adrenal insufficiency is suspected, confirm the diagnosis with diagnostic testing as soon as possible. If adrenal insufficiency is diagnosed, treat with physiologic replacement doses of corticosteroids. Wean the patient off of the opioid to allow adrenal function to recover and continue corticosteroid treatment until adrenal function recovers. Other opioids may be tried as some cases reported use of a different opioid without recurrence of adrenal insufficiency. The information available does not identify any particular opioids as being more likely to be associated with adrenal insufficiency.

5.21 Drug/Laboratory Test Interactions

Because opioid agonists may increase biliary tract pressure, with resultant increase in plasma amylase or lipase levels, determination of these enzyme levels may be unreliable for 24 hours after administration of a dose of Promethazine HCl and Codeine Phosphate Oral Solution.

The following laboratory tests may be affected in patients who are receiving promethazine:

Pregnancy Tests: Diagnostic pregnancy tests based on immunological reactions between HCG and anti-HCG may result in false-negative or false-positive interpretations.

Glucose Tolerance Test: An increase in blood glucose has been reported in patients receiving promethazine.

6 ADVERSE REACTIONS

The following serious adverse reactions are described, or described in greater detail, in other sections:

- Addiction, abuse, and misuse [see Warnings and Precautions (5.1), Drug Abuse and Dependence (9.3)]
- Life-threatening respiratory depression [see Warnings and Precautions (5.2,5.3, 5.4, 5.5, 5.6), Overdosage (10)]
- Ultra-rapid metabolism of codeine and other risk factors for life-threatening respiratory depression in children [see Warnings and Precautions (5.3)]
- Accidental overdose and death due to medication errors [see Warnings and Precautions (5.7)]
- Decreased mental alertness with impaired mental and/or physical abilities [see Warnings and Precautions (5.8)]
- Interactions with benzodiazepines and other CNS depressants [see Warnings and Precautions (5.10)]
- Paralytic ileus, gastrointestinal adverse reactions [see Warnings and Precautions (5.11)]
- Increased intracranial pressure [see Warnings and Precautions (5.12)]
- Obscured clinical course in patients with head injuries [see Warnings and Precautions (5.12)]
- Neuroleptic Malignant Syndrome [see Warnings and Precautions (5.13)]
- Paradoxical reactions, including dystonias [see Warnings and Precautions (5.14)]
- Seizures [see Warnings and Precautions (5.15)]
- Interactions with MAOI [see Warnings and Precautions (5.16)]
- Bone marrow suppression [see Warnings and Precautions (5.17)]
- Severe hypotension [see Warnings and Precautions (5.18)]
- Neonatal Opioid Withdrawal Syndrome [see Warnings and Precautions (5.19)]
- Adrenal insufficiency [see Warnings and Precautions (5.20)]

The following adverse reactions have been identified during clinical studies, in the literature, or during postapproval use of codeine and/or promethazine. Because these reactions may be reported voluntarily from a population of uncertain size, it is not always possible to reliably estimate their frequency or establish a causal relationship to drug exposure.

The most common adverse reactions to Promethazine HCl and Codeine Phosphate Oral Solution include: Sedation (somnolence, mental clouding, lethargy), impaired mental and physical performance, lightheadedness, dizziness, headache, dry mouth, nausea, vomiting, constipation, shortness of breath, sweating.

Other reactions include:

Anaphylaxis: Anaphylaxis has been reported with codeine, one of the ingredients in Promethazine HCl and Codeine Phosphate Oral Solution.

Body as a whole: Coma, death, fatigue, falling injuries, lethargy.

Cardiovascular: Peripheral edema, increased blood pressure, decreased blood pressure, tachycardia, chest pain, palpitation, syncope, orthostatic hypotension, prolonged QT interval, hot flush.

Central Nervous System: Ataxia, diplopia, facial dyskinesia, insomnia, migraine, increased intracranial pressure, seizure, tinnitus, tremor, vertigo.

Dermatologic: Flushing, hyperhidrosis, photosensitivity, pruritus, rash, urticaria.

Endocrine/Metabolic: Cases of serotonin syndrome, a potentially life-threatening condition, have been reported during concomitant use of opioids with serotonergic drugs. Cases of adrenal insufficiency have been reported with opioid use, more often following greater than one month of use. Cases of androgen deficiency have occurred with chronic use of opioids [see Clinical Pharmacology (12.2)].

Gastrointestinal: Abdominal pain, bowel obstruction, decreased appetite, diarrhea, difficulty swallowing, dry mouth, GERD, indigestion, jaundice, pancreatitis, paralytic ileus, biliary tract spasm (spasm of the sphincter of Oddi).

Genitourinary: Urinary tract infection, ureteral spasm, spasm of vesicle sphincters, urinary retention.

Hematologic: Bone marrow suppression, agranulocytosis, aplastic anemia, and thrombocytopenia have been reported.

Laboratory: Increases in serum amylase.

Musculoskeletal: Arthralgia, backache, muscle spasm.

Ophthalmic: Blurred vision, miosis (constricted pupils), visual disturbances.

Paradoxical Reactions: Dystonias, torticollis, tongue protrusion, hyperexcitability, and abnormal movements have been reported following a single administration of promethazine.

Psychiatric: Agitation, anxiety, confusion, fear, dysphoria, depression, hallucinations.

Reproductive: Hypogonadism, infertility.

Respiratory: Apnea, bronchitis, cough, dry nose, dry throat, dyspnea, nasal congestion, nasopharyngitis, respiratory depression, sinusitis, thickening of bronchial secretions, tightness of chest and wheezing, upper respiratory tract infection.

Other: Drug abuse, drug dependence, Neuroleptic Malignant Syndrome, opioid withdrawal syndrome.

Hypoglycemia: Cases of hypoglycemia have been reported in patients taking opioids. Most reports were in patients with at least one predisposing risk factor (e.g., diabetes).

7 DRUG INTERACTIONS

No specific drug interaction studies have been conducted with Promethazine HCl and Codeine Phosphate Oral Solution.

7.1 Inhibitors of CYP3A4

The concomitant use of Promethazine HCl and Codeine Phosphate Oral Solution with CYP3A4 inhibitors, such as macrolide antibiotics (e.g., erythromycin), azole-antifungal agents (e.g. ketoconazole), or protease inhibitors (e.g., ritonavir), may result in an increase in codeine plasma concentrations with subsequently greater metabolism by cytochrome CYP2D6, resulting in greater morphine levels, which could increase or prolong adverse reactions and may cause potentially fatal respiratory depression, particularly when an inhibitor is added after a stable dose of Promethazine HCl and Codeine Phosphate Oral Solution is achieved [see Warnings and Precautions (5.9)]. After stopping a CYP3A4 inhibitor, as the effects of the inhibitor decline, it may result in lower codeine levels, greater norcodeine levels, and less metabolism via CYP2D6 with resultant lower morphine levels [see Clinical Pharmacology (12.3)], resulting in decreased opioid efficacy or a withdrawal syndrome in patients who had developed physical dependence to codeine.

Avoid the use of Promethazine HCl and Codeine Phosphate Oral Solution while taking a CYP3A4 inhibitor. If concomitant use is necessary, monitor patients for respiratory depression and sedation at frequent intervals.

7.2 CYP3A4 Inducers

The concomitant use of Promethazine HCl and Codeine Phosphate Oral Solution and CYP3A4 inducers, such as rifampin, carbamazepine, or phenytoin, can result in lower codeine levels, greater norcodeine levels, and less metabolism via 2D6 with resultant lower morphine levels [see Clinical Pharmacology (12.3)], resulting in decreased efficacy or onset of a withdrawal syndrome in patients who have developed physical dependence [see Warnings and Precautions (5.9)]. After stopping a CYP3A4 inducer, as the effects of the inducer decline, codeine plasma concentrations may increase with subsequently greater metabolism by cytochrome CYP2D6, resulting in greater morphine levels [see Clinical Pharmacology (12.3)], which could increase or prolong both the therapeutic effects and adverse reactions, and may cause serious respiratory depression.

Avoid the use of Promethazine HCl and Codeine Phosphate Oral Solution in patients who are taking CYP3A4 inducers. If concomitant use of a CYP3A4 inducer is necessary, follow the patient for reduced efficacy.

7.3 Inhibitors of CYP2D6

Codeine is metabolized by CYP2D6 to form morphine. The concomitant use of Promethazine HCl and Codeine Phosphate Oral Solution and CYP2D6 inhibitors, such as paroxetine, fluoxetine, bupropion, or quinidine, can increase the plasma concentration of codeine, but can decrease the plasma concentration of active metabolite morphine, which could result in reduced efficacy [see Clinical Pharmacology (12.3)].

After stopping a CYP2D6 inhibitor, as the effects of the inhibitor decline, the codeine plasma concentration will decrease but the active metabolite morphine plasma concentration will increase, which could increase or prolong adverse reactions and may cause potentially fatal respiratory depression [see Clinical Pharmacology (12.3)].

Avoid the use of Promethazine HCl and Codeine Phosphate Oral Solution in patients who are taking inhibitors of CYP2D6.

7.4 Benzodiazepines, and Other CNS Depressants

Due to additive pharmacologic effect, the concomitant use of benzodiazepines or other CNS depressants, including alcohol, other sedatives/hypnotics, anxiolytics, tranquilizers, muscle relaxants, general anesthetics, antipsychotics, and other opioids, can increase the risk of hypotension, respiratory depression, profound sedation, coma, and death. Avoid the use of Promethazine HCl and Codeine Phosphate Oral Solution in patients who are taking benzodiazepines or other CNS depressants. [see Warnings and Precautions (5.10)].

7.5 Serotonergic Drugs

The concomitant use of opioids with other drugs that affect the serotonergic neurotransmitter system has resulted in serotonin syndrome. If concomitant use is warranted, carefully observe the patient, particularly during treatment initiation. Discontinue Promethazine HCl and Codeine Phosphate Oral Solution if serotonin syndrome is suspected.

7.6 Monoamine Oxidase Inhibitors (MAOIs)

Promethazine HCl and Codeine Phosphate Oral Solution is contraindicated in patients who are taking MAOIs (i.e., certain drugs used for depression, psychiatric or emotional conditions, or Parkinson’s disease) or have taken MAOIs within 14 days [see Contraindications (4)].

MAOI interactions with opioids may manifest as serotonin syndrome or opioid toxicity (e.g., respiratory depression, coma) [see Warnings and Precautions (5.16)].

Drug interactions, including an increased incidence of extrapyramidal effects, have been reported when some MAOI and phenothiazines are used concomitantly.

7.7 Muscle Relaxants

Codeine may enhance the neuromuscular blocking action of skeletal muscle relaxants and produce an increased degree of respiratory depression. Avoid the use of Promethazine HCl and Codeine Phosphate Oral Solution in patients taking muscle relaxants. If concomitant use is necessary, monitor patients for signs of respiratory depression that may be greater than otherwise expected.

7.8 Diuretics

Opioids can reduce the efficacy of diuretics by inducing the release of antidiuretic hormone. Monitor patients for signs of diminished diuresis and/or effects on blood pressure and increase the dosage of the diuretic as needed.

7.9 Anticholinergic Drugs

The concomitant use of anticholinergic drugs with Promethazine HCl and Codeine Phosphate Oral Solution may increase risk of urinary retention and/or severe constipation, which may lead to paralytic ileus [see Warnings and Precautions (5.11)]. Monitor patients for signs of urinary retention or reduced gastric motility when Promethazine HCl and Codeine Phosphate Oral Solution is used concomitantly with anticholinergic drugs.

Additive adverse effects resulting from cholinergic blockade (e.g., xerostomia, blurred vision, or constipation) may occur when anticholinergic drugs are administered with promethazine].

8 USE IN SPECIFIC POPULATIONS

8.1 Pregnancy

Risk Summary

Promethazine HCl and Codeine Phosphate Oral Solution is not recommended for use in pregnant women, including during or immediately prior to labor.

Prolonged use of opioids during pregnancy may cause neonatal opioid withdrawal syndrome [see Warnings and Precautions (5.19), Clinical Considerations].

There are no available data with Promethazine HCl and Codeine Phosphate Oral Solution use in pregnant women to inform a drug-associated risk for adverse developmental outcomes. Published studies with codeine have reported inconsistent findings and have important methodological limitations (see Data). There are reports of respiratory depression when codeine is used during labor and delivery (see Clinical Considerations).

Reproductive toxicity studies have not been conducted with Promethazine HCl and Codeine Phosphate Oral Solution; however, studies are available with individual active ingredients (see Data).

In animal reproduction studies, codeine administered by the oral route to pregnant rats during the period of organogenesis increased resorptions and decreased fetal weights at a dose approximately 25 times the maximum recommended human dose (MRHD) in the presence of maternal toxicity (see Data).

For pregnant mice and rats that received promethazine at doses 0.2 and 3-6 times the MRHD, during various periods of gestation, there were findings of increased fetal resorptions and skeletal fragility, decreased pup weight, and developmental delays of pups (see Data).

Based on the animal data, advise pregnant women of the potential risk to a fetus.

The estimated background risk of major birth defects and miscarriage for the indicated population is unknown. All pregnancies have a background risk of birth defect, loss, or other adverse outcomes. In the U.S. general population, the estimated background risk of major birth defects and miscarriage in clinically recognized pregnancies is 2 to 4% and 15 to 20%, respectively.

Clinical Considerations

Fetal/Neonatal Adverse Reactions

Prolonged use of opioid analgesics during pregnancy for medical or nonmedical purposes can result in physical dependence in the neonate and neonatal opioid withdrawal syndrome shortly after birth.

Neonatal opioid withdrawal syndrome presents as irritability, hyperactivity and abnormal sleep pattern, high pitched cry, tremor, vomiting, diarrhea and failure to gain weight. The onset, duration, and severity of neonatal opioid withdrawal syndrome vary based on the specific opioid used, duration of use, timing and amount of last maternal use, and rate of elimination of the drug by the newborn. Observe newborns for symptoms of neonatal opioid withdrawal syndrome and manage accordingly [see Warnings and Precautions (5.19)].

Labor or Delivery

Opioids cross the placenta and may produce respiratory depression and psycho-physiologic effects in neonates. An opioid antagonist, such as naloxone, must be available for reversal of opioid-induced respiratory depression in the neonate. Opioids, including Promethazine HCl and Codeine Phosphate Oral Solution, can prolong labor through actions which temporarily reduce the strength, duration, and frequency of uterine contractions.

However, this effect is not consistent and may be offset by an increased rate of cervical dilation, which tends to shorten labor. Monitor neonates exposed to opioids during labor for signs of excess sedation and respiratory depression.

Data

Human Data

Published data from case-control and observational studies on codeine use during pregnancy are inconsistent in their findings. Some studies of codeine exposure showed an increased risk of overall congenital malformations while others did not. An increased risk of specific malformations with codeine exposure such as respiratory malformations, spina bifida and congenital heart defects were reported in some studies.

The majority of studies examining the use of promethazine in pregnancy did not find an association with an increased risk of congenital anomalies. In the few studies reporting an association, no consistent pattern of malformations was noted.

Most of the studies, both positive and negative, were limited by small sample size, recall bias and lack of information regarding dose and timing of exposure.

Animal Data

Reproductive toxicity studies have not been conducted with Promethazine HCl and Codeine Phosphate Oral Solution; however, studies are available with individual active ingredients.

Codeine

In an embryofetal development study in pregnant rats dosed throughout the period of organogenesis, codeine increased resorptions and decreased fetal weights at a dose approximately 25 times the MRHD (on a mg/m^2 basis with a maternal oral dose of 120 mg/kg/day); however, these effects occurred in the presence of maternal toxicity. In embryofetal development studies with pregnant rabbits and mice dosed throughout the period of organogenesis, codeine produced no adverse developmental effects at doses approximately 15 and 65 times, respectively, the MRHD (on a mg/m^2 basis with maternal oral doses of 30 mg/kg/day in rabbits and 600 mg/kg/day in mice).

Promethazine

In pregnant mice dosed during the period of implantation from gestation days 1 to 5, promethazine increased resorption at doses approximately 0.2 times the MRHD (on a mg/m^2 basis with maternal intraperitoneal and subcutaneous doses up to 1 mg/kg/day).

In pregnant rats dosed during the period of organogenesis from gestation days 5 to 16, promethazine hydrochloride induced complete resorption at doses approximately 6 times the MRHD (on a mg/m^2 basis with maternal oral doses up to 20 mg/kg/day).

In pregnant rats dosed during the period of organogenesis from gestation days 7 to 13, promethazine resulted in skeletal fragility of pups at doses approximately 3 times the MRHD (on a mg/m^2 basis with maternal oral doses up to 10 mg/kg/day).

In pregnant rats dosed during the period of organogenesis from gestation days 10 to 12, promethazine resulted in decreased weight and delays in initial occurrence of behavioral/reflex of pups at doses approximately 3 times the MRHD (on a mg/m^2 basis with maternal oral doses up to 10 mg/kg/day).

The relevance of these findings to humans is unclear.

8.2 Lactation

Risk Summary
Because of the potential for serious adverse reactions, including excess sedation, respiratory depression, and death in a breastfed infant, advise patients that breastfeeding is not recommended during treatment with Promethazine HCl and Codeine Phosphate Oral Solution [see Warnings and Precautions (5.3)].

There are no data on the presence of Promethazine HCl and Codeine Phosphate Oral Solution in human milk, the effects of Promethazine HCl and Codeine Phosphate Oral Solution on the breastfed infant, or the effects of Promethazine HCl and Codeine Phosphate Oral Solution on milk production; however, data are available with codeine and promethazine.

Codeine
Codeine and its active metabolite, morphine, are present in human milk. There are published studies and cases that have reported excessive sedation, respiratory depression and death (in one infant) in infants exposed to codeine via breast milk. Women who are ultra-rapid metabolizers of codeine achieve higher than expected serum levels of morphine, potentially leading to higher levels of morphine in breast milk that can be dangerous in their breastfed infants. In women with normal codeine metabolism (normal CYP2D6 activity), the amount of codeine secreted into human milk is low and dose-dependent. There is no information on the effects of the codeine on milk production.

Promethazine
There are no data on the presence of promethazine in human milk. However, direct oral administration of promethazine has been associated with respiratory depression, including fatalities, in pediatric patients [see Warnings and Precautions (5.4)]. Promethazine has been shown to decrease basal prolactin levels in non-nursing women, and therefore may affect milk production.

Clinical Considerations
Infants exposed to Promethazine HCl and Codeine Phosphate Oral Solution through breast milk should be monitored for excess sedation and respiratory depression. Withdrawal symptoms can occur in breastfed infants when maternal administration of an opioid is stopped, or when breastfeeding is stopped.

8.3 Females and Males of Reproductive Potential

Infertility
Chronic use of opioids, such as codeine, a component of Promethazine HCl and Codeine Phosphate Oral Solution, may cause reduced fertility in females and males of reproductive potential. It is not known whether these effects on fertility are reversible [see Adverse Reactions (6),Clinical Pharmacology (12.2)].

8.4 Pediatric Use

Promethazine HCl and Codeine Phosphate Oral Solution is not indicated for use in patients younger than 18 years of age because the benefits of symptomatic treatment of cough associated with allergies or the common cold do not outweigh the risks for use of codeine in these patients [see Indications (1), Warnings and Precautions (5.5)]. Life-threatening respiratory depression and death have occurred in children who received codeine [see Warnings and Precautions (5.2)]. In most of the reported cases, these events followed tonsillectomy and/or adenoidectomy, and many of the children had evidence of being ultra-rapid metabolizers of codeine (i.e., multiple copies of the gene for cytochrome P450 isoenzyme 2D6 or high morphine concentrations). Children with sleep apnea may be particularly sensitive to the respiratory depressant effects of codeine.

Life-threatening respiratory depression and death have also occurred in children who received promethazine [see Warnings and Precautions (5.4)].

Because of the risk of life-threatening respiratory depression and death:

- Promethazine HCl and Codeine Phosphate Oral Solution is contraindicated for all children younger than 12 years of age [see Contraindications (4)].
- Promethazine HCl and Codeine Phosphate Oral Solution is contraindicated for post-operative management in pediatric patients younger than 18 years of age following tonsillectomy and/or adenoidectomy [see Contraindications (4)].
- Avoid the use of Promethazine HCl and Codeine Phosphate Oral Solution in adolescents 12 to 18 years of age who have other risk factors that may increase their sensitivity to the respiratory depressant effects of codeine unless the benefits outweigh the risks. Risk factors include conditions associated with hypoventilation, such as postoperative status, obstructive sleep apnea, obesity, severe pulmonary disease, neuromuscular disease, and concomitant use of other medications that cause respiratory depression [see Warnings and Precautions (5.3, 5.6)].

8.5 Geriatric Use

Clinical studies have not been conducted with Promethazine HCl and Codeine Phosphate Oral Solution in geriatric populations.

Use caution when considering the use of Promethazine HCl and Codeine Phosphate Oral Solution in patients 65 years of age or older. Elderly patients may have increased sensitivity to codeine; greater frequency of decreased hepatic, renal, or cardiac function; or concomitant disease or other drug therapy [see Warnings and Precautions (5.6)].

Respiratory depression is the chief risk for elderly patients treated with opioids, including Promethazine HCl and Codeine Phosphate Oral Solution. Respiratory depression has occurred after large initial doses of opioids were administered to patients who were not opioid-tolerant or when opioids were co-administered with other agents that depress respiration [see Warnings and Precautions (5.6, 5.10)].

Codeine is known to be substantially excreted by the kidney, and the risk of adverse reactions to this drug may be greater in patients with impaired renal function. Because elderly patients are more likely to have decreased renal function, monitor these patients closely for respiratory depression, sedation, and hypotension.

8.6 Renal Impairment

The pharmacokinetics of Promethazine HCl and Codeine Phosphate Oral Solution has not been characterized in patients with renal impairment. Codeine pharmacokinetics may be altered in patients with renal failure. Clearance may be decreased and the metabolites may accumulate to much higher plasma levels in patients with renal failure as compared to patients with normal renal function. Promethazine HCl and Codeine Phosphate Oral Solution should be used with caution in patients with severe impairment of renal function, and patients should be monitored closely for respiratory depression, sedation, and hypotension.

8.7 Hepatic Impairment

No formal studies have been conducted in patients with hepatic impairment so the pharmacokinetics of Promethazine HCl and Codeine Phosphate Oral Solution in this patient population are unknown. Promethazine HCl and Codeine Phosphate Oral Solution should be used with caution in patients with impairment of hepatic function, and patients should be monitored closely for respiratory depression, sedation, and hypotension.

9 DRUG ABUSE AND DEPENDENCE

9.1 Controlled Substance

Promethazine HCl and Codeine Phosphate Oral Solution contains codeine, a Schedule V controlled substance.

9.2 Abuse

Codeine
Promethazine HCl and Codeine Phosphate Oral Solution contains codeine, a substance with a high potential for abuse similar to other opioids including morphine and codeine. Promethazine HCl and Codeine Phosphate Oral Solution can be abused and is subject to misuse, addiction, and criminal diversion [see Warnings and Precautions (5.1)].

All patients treated with opioids require careful monitoring for signs of abuse and addiction, since use of opioid analgesic and antitussive products carries the risk of addiction even under appropriate medical use.

Prescription drug abuse is the intentional non-therapeutic use of a prescription drug, even once, for its rewarding psychological or physiological effects.

Drug addiction is a cluster of behavioral, cognitive, and physiological phenomena that develop after repeated substance use and includes: a strong desire to take the drug, difficulties in controlling its use, persisting in its use despite harmful consequences, a higher priority given to drug use than to other activities and obligations, increased tolerance, and sometimes a physical withdrawal.

“Drug-seeking” behavior is very common in persons with substance use disorders. Drug-seeking tactics include emergency calls or visits near the end of office hours, refusal to undergo appropriate examination, testing, or referral, repeated “loss” of prescriptions, tampering with prescriptions, and reluctance to provide prior medical records or contact information for other treating health care provider(s). “Doctor shopping” (visiting multiple prescribers to obtain additional prescriptions) is common among drug abusers and people suffering from untreated addiction. Preoccupation with achieving adequate pain relief can be appropriate behavior in a patient with poor pain control.

Abuse and addiction are separate and distinct from physical dependence and tolerance. Health care providers should be aware that addiction may not be accompanied by concurrent tolerance and symptoms of physical dependence in all addicts. In addition, abuse of opioids can occur in the absence of true addiction.

Promethazine HCl and Codeine Phosphate Oral Solution, like other opioids, can be diverted for non-medical use into illicit channels of distribution. Careful record-keeping of prescribing information, including quantity, frequency, and renewal requests, as required by state and federal law, is strongly advised.

Proper assessment of the patient, proper prescribing practices, periodic re-evaluation of therapy, and proper dispensing and storage are appropriate measures that help to limit abuse of opioid drugs.

Risks Specific to Abuse of Promethazine HCl and Codeine Phosphate Oral Solution
Promethazine HCl and Codeine Phosphate Oral Solution is for oral use only. Abuse of Promethazine HCl and Codeine Phosphate Oral Solution poses a risk of overdose and death. The risk is increased with concurrent use of Promethazine HCl and Codeine Phosphate Oral Solution with alcohol and other central nervous system depressants [see Warnings and Precautions (5.10)].

Parenteral drug abuse is commonly associated with transmission of infectious diseases such as hepatitis and HIV.

9.3 Dependence

Psychological dependence, physical dependence, and tolerance may develop upon repeated administration of opioids; therefore, Promethazine HCl and Codeine Phosphate Oral Solution should be prescribed and administered for the shortest duration that is consistent with individual patient treatment goals and patients should be reevaluated prior to refills [see Dosage and Administration (2.3), Warnings and Precautions (5.1)].

Physical dependence, the condition in which continued administration of the drug is required to prevent the appearance of a withdrawal syndrome, assumes clinically significant proportions only after several weeks of continued oral opioid use, although some mild degree of physical dependence may develop after a few days of opioid therapy.

If Promethazine HCl and Codeine Phosphate Oral Solution is abruptly discontinued in a physically-dependent patient, a withdrawal syndrome may occur. Withdrawal also may be precipitated through the administration of drugs with opioid antagonist activity (e.g., naloxone, nalmefene), mixed agonist/antagonist analgesics (e.g., pentazocine, butorphanol, nalbuphine), or partial agonists (e.g., buprenorphine). Some or all of the following can characterize this syndrome: restlessness, lacrimation, rhinorrhea, yawning, perspiration, chills, myalgia, and mydriasis. Other signs and symptoms also may develop, including irritability, anxiety, backache, joint pain, weakness, abdominal cramps, insomnia, nausea, anorexia, vomiting, diarrhea, or increased blood pressure, respiratory rate, or heart rate.

Infants born to mothers physically dependent on opioids will also be physically dependent and may exhibit respiratory difficulties and withdrawal signs [see Use in Specific Populations (8.1)].

10 OVERDOSAGE

Clinical Presentation

Codeine
Acute overdose with codeine is characterized by respiratory depression (a decrease in respiratory rate and/or tidal volume, Cheyne-Stokes respiration, cyanosis), extreme somnolence progressing to stupor or coma, skeletal muscle flaccidity, cold and clammy skin, constricted pupils, and, in some cases, pulmonary edema, bradycardia, partial or complete airway obstruction, atypical snoring, hypotension, hypoglycemia, circulatory collapse, cardiac arrest, and death.

Codeine may cause miosis, even in total darkness. Pinpoint pupils are a sign of opioid overdose but are not pathognomonic (e.g., pontine lesions of hemorrhagic or ischemic origin may produce similar findings). Marked mydriasis rather than miosis may be seen with hypoxia in overdose situations [see Clinical Pharmacology (12.2)].

Promethazine

Signs and symptoms of overdosage with promethazine range from mild depression of the central nervous system and cardiovascular system to profound hypotension, respiratory depression, unconsciousness and sudden death. Other reported reactions include hyperreflexia, hypertonia, ataxia, athetosis and extensor-plantar reflexes (Babinski reflex).

Stimulation may be evident, especially in children and geriatric patients. Convulsions may rarely occur. A paradoxical reaction has been reported in children receiving single doses of 75 mg to 125 mg orally, characterized by hyperexcitability and nightmares.

Atropine-like signs and symptoms (dry mouth, fixed dilated pupils, flushing, tachycardia, hallucinations, gastrointestinal symptoms, convulsions, urinary retention, cardiac arrhythmias and coma) may be observed.

Impaired secretion from sweat glands following toxic doses of drugs with anticholinergic side effects may predispose to hyperthermia.

Treatment of Overdose
Treatment of overdosage is driven by the overall clinical presentation, and consists of discontinuation of Promethazine HCl and Codeine Phosphate Oral Solution together with institution of appropriate therapy. Give primary attention to the reestablishment of adequate respiratory exchange through provision of a patent and protected airway and the institution of assisted or controlled ventilation. Employ other supportive measures (including oxygen and vasopressors) in the management of circulatory shock and pulmonary edema as indicated. Cardiac arrest or arrhythmias will require advanced life-support techniques. Gastric emptying may be useful in removing unabsorbed drug.

The opioid antagonists, naloxone and nalmefene, are specific antidotes for respiratory depression resulting from opioid overdose. For clinically significant respiratory or circulatory depression secondary to codeine overdose, administer an opioid antagonist. An antagonist should not be administered in the absence of clinically significant respiratory depression. Because the duration of opioid reversal is expected to be less than the duration of action of codeine in Promethazine HCl and Codeine Phosphate Oral Solution, carefully monitor the patient until spontaneous respiration is reliably reestablished. If the response to an opioid antagonist is suboptimal or only brief in nature, administer additional antagonist as directed by the product’s prescribing information. The respiratory depressant effects of promethazine are not reversed by opioid antagonists, such as naloxone.

Because of the potential for promethazine to reverse epinephrine’s vasopressor effect, epinephrine should NOT be used to treat hypotension associated with promethazine overdose.

Hemodialysis is not routinely used to enhance the elimination of codeine or promethazine from the body.

11 DESCRIPTION

Promethazine HCl and Codeine Phosphate Oral Solution contains codeine, an opioid agonist, and promethazine, a phenothiazine.

Each 5 mL of Promethazine HCl and Codeine Phosphate Oral Solution contains 10 mg of codeine phosphate and 6.25 mg of promethazine hydrochloride for oral administration.

Promethazine HCl and Codeine Phosphate Oral Solution has a pH between 4.8 and 5.4 and contains alcohol 8% (v/v).

Promethazine HCl and Codeine Phosphate Oral Solution also contains the following inactive ingredients: anhydrous citric acid, ascorbic acid, D&C Red # 33, edetate disodium, FD&C Blue #1, methylparaben, peach-mint flavor, propylene glycol, propylparaben, purified water, saccharin sodium, sodium benzoate, sodium citrate anhydrous, sodium metabisulfite, sucrose.

Codeine Phosphate
The chemical name for codeine phosphate is 7,8-Didehydro-4, 5α-epoxy-3-methoxy-17-methylmorphinan-6α-ol phosphate (1:1) (salt) hemihydrate. Codeine is one of the naturally occurring phenanthrene alkaloids of opium derived from the opium poppy, it is classified pharmacologically as a narcotic analgesic. The phosphate salt of codeine occurs as white, needle-shaped crystals or white crystalline powder. Codeine phosphate is freely soluble in water and slightly soluble in alcohol. The molecular weight is 406.37. Its molecular formula is C18H21NO3•H3PO4 • ½ H2O, and it has the following chemical structure.

Promethazine Hydrochloride
The chemical name for promethazine hydrochloride, a phenothiazine derivative, is (±)-10-[2-(Dimethylamino)propyl] phenothiazine monohydrochloride. Promethazine hydrochloride occurs as a white to faint yellow, practically odorless, crystalline powder which slowly oxidizes and turns blue on prolonged exposure to air. It is soluble in water and freely soluble in alcohol. The molecular weight is 320.88. Its molecular formula is C17H20N2S•HCl, and it has the following chemical structure.

12 CLINICAL PHARMACOLOGY

12.1 Mechanism of Action

Codeine
Codeine is an opioid agonist relatively selective for the mu-opioid receptor, but with a much weaker affinity than morphine. The analgesic and antitussive properties of codeine have been speculated to come from its conversion to morphine. The precise mechanism of action of codeine and other opiates is not known; however, codeine is believed to act centrally on the cough center. In excessive doses, codeine will depress respiration.

Promethazine

Promethazine is a phenothiazine derivative, which differs structurally from the antipsychotic phenothiazines by the presence of a branched side chain and no ring substitution. Promethazine possesses antihistamine (H1 receptor antagonist), antiemetic, sedative, and anticholinergic effects. It prevents released histamine from dilating capillaries and causing edema of the respiratory mucosa.

12.2 Pharmacodynamics

Codeine

Effects on the Central Nervous System
Codeine produces respiratory depression by direct action on brain stem respiratory centers. The respiratory depression involves a reduction in the responsiveness of the brain stem respiratory centers to both increases in carbon dioxide tension and to electrical stimulation.

Codeine causes miosis, even in total darkness. Pinpoint pupils are a sign of opioid overdose but are not pathognomonic (e.g., pontine lesions of hemorrhagic or ischemic origins may produce similar findings). Marked mydriasis rather than miosis may be seen due to hypoxia in overdose situations.

Effects on the Gastrointestinal Tract and Other Smooth Muscle
Codeine causes a reduction in motility associated with an increase in smooth muscle tone in the antrum of the stomach and duodenum. Digestion of food in the small intestine is delayed and propulsive contractions are decreased. Propulsive peristaltic waves in the colon are decreased, while tone may be increased to the point of spasm resulting in constipation. Other opioid-induced effects may include a reduction in biliary and pancreatic secretions, spasm of sphincter of Oddi, and transient elevations in serum amylase.

Effects on the Cardiovascular System
Codeine produces peripheral vasodilation which may result in orthostatic hypotension or syncope. Manifestations of histamine release and/or peripheral vasodilation may include pruritus, flushing, red eyes and sweating and/or orthostatic hypotension.

Effects on the Endocrine System
Opioids inhibit the secretion of adrenocorticotropic hormone (ACTH), cortisol, and luteinizing hormone (LH) in humans [see Adverse Reactions (6)]. They also stimulate prolactin, growth hormone (GH) secretion, and pancreatic secretion of insulin and glucagon.

Chronic use of opioids may influence the hypothalamic-pituitary-gonadal axis, leading to androgen deficiency that may manifest as low libido, impotence, erectile dysfunction, amenorrhea, or infertility. The causal role of opioids in the clinical syndrome of hypogonadism is unknown because the various medical, physical, lifestyle, and psychological stressors that may influence gonadal hormone levels have not been adequately controlled for in studies conducted to date [see Adverse Reactions (6)].

Effects on the Immune System
Opioids have been shown to have a variety of effects on components of the immune system in in vitro and animal models. The clinical significance of these findings is unknown. Overall, the effects of opioids appear to be modestly immunosuppressive.

Concentration–Adverse Reaction Relationships

There is a relationship between increasing codeine plasma concentration and increasing frequency of dose-related opioid adverse reactions such as nausea, vomiting, CNS effects, and respiratory depression. In opioid-tolerant patients, the situation may be altered by the development of tolerance to opioid-related adverse reactions.

Promethazine
Promethazine competitively antagonize H1 receptors located in most of the smooth muscle including the gastrointestinal tract, uterus, large blood vessels and bronchial muscle. Actions of histamine on H1 receptors increases capillary permeability and edema formation, flare and pruritus.

12.3 Pharmacokinetics

Absorption
Codeine is absorbed from the gastrointestinal tract with maximum plasma concentration occurring 60 minutes post administration. The presence of a high-fat, high-calorie meal did not significantly impact the PK of codeine.

Promethazine is well absorbed from the gastrointestinal tract. Clinical effects are apparent within 20 minutes after oral administration and generally last four to six hours, although they may persist as long as 12 hours.

Distribution
Codeine has been reported to have an apparent volume of distribution of approximately 3 to 6 L/kg, indicating extensive distribution of the drug into tissues. Codeine has low plasma protein binding with about 7 to 25% of codeine bound to plasma proteins. Codeine passes the blood brain barrier and the placental barrier. Small amounts of codeine and its metabolite, morphine, are transferred to human breast milk.

Promethazine is widely distributed in body tissues. Promethazine has high protein binding with about 80 to 93% of promethazine bound to plasma proteins. Promethazine passes the blood brain barrier and the placental barrier.

Elimination

Metabolism
Codeine is metabolized by conjugation with glucuronic acid to codeine-6-glucuronide (about 70 to 80%), by O-demethylation to morphine (about 5 to 10%), and by N-demethylation to norcodeine (about 10%). UDP-glucuronosyltransferase (UGT) 2B7 and 2B4 are the major enzymes mediating glucuronidation of codeine to C6G. Cytochrome P450 2D6 is the major enzyme responsible for conversion of codeine to morphine and P450 3A4 is the major enzyme mediating conversion of codeine to norcodeine. Morphine and norcodeine are further metabolized by conjugation with glucuronic acid. The glucuronide metabolites of morphine are morphine-3-glucuronide (M3G) and morphine-6-glucuronide (M6G). Morphine and its M6 glucuronide conjugate are pharmacologically active. Whether C6G has pharmacological activity is unknown. Norcodeine and M3 glucuronide conjugate of morphine are generally not considered to be pharmacologically active.

Promethazine is metabolized by the liver to a variety of inactive metabolites such as sulfoxides of promethazine, N-demethylpromethazine and other glucuronides.

Excretion
Approximately 90% of the total dose of codeine is excreted through the kidneys, of which approximately 10% is unchanged codeine. Plasma half-lives of codeine and its metabolites have been reported to be approximately 3 hours.

Promethazine has an elimination half-life of 10-14 hours, with excretion of metabolites appearing in the urine and feces. The sulfoxides of promethazine and N-demethylpromethazine are the predominant metabolites appearing in the urine.

13 NONCLINICAL TOXICOLOGY

13.1 Carcinogenesis, Mutagenesis, Impairment of Fertility

Carcinogenicity, mutagenicity, and fertility studies have not been conducted with Promethazine HCl and Codeine Phosphate Oral Solution; however, published information is available for the individual active ingredients.

Codeine
Carcinogenicity studies were conducted with codeine. Two-year studies in F344/N rats and B6C3F1 mice were conducted to assess the carcinogenic potential of codeine. No evidence of tumorigenicity was observed in male and female rats at codeine dietary doses up to 70 and 80 mg/kg/day (approximately equivalent to 15 and 20 times, the MRHD on a mg/m^2 basis, respectively). No evidence of tumorigenicity was observed in male and female mice at codeine dietary doses up to 400 mg/kg/day (approximately equivalent to 45 times the MRHD on a mg/m^2 basis).

Codeine was not mutagenic in the in vitro bacterial reverse mutation assay or clastogenic in the in vitro Chinese hamster ovary (CHO) cell chromosomal aberration assay.

Fertility studies with codeine have not been conducted.

Promethazine

Carcinogenicity studies were conducted with promethazine hydrochloride. Two-year studies in F344/N rats and B6C3F1 mice were conducted to assess the carcinogenic potential of promethazine hydrochloride. No evidence of tumorigenicity was observed in male and female rats at promethazine hydrochloride oral doses up to 33 mg/kg/day for 5 days/week (approximately equivalent to 10 times the MRHD on a mg/m^2 basis). No evidence of tumorigenicity was observed in male and female mice at promethazine hydrochloride oral doses up to 45 and 15 mg/kg/day for 5 days/week (approximately equivalent to 7 and 2 times the MRHD on a mg/m^2 basis, respectively).

Promethazine hydrochloride was not mutagenic in the in vitro bacterial reverse mutation assay or clastogenic in the in vitro Chinese hamster ovary (CHO) cell chromosomal aberration assay.

Fertility studies with promethazine have not been conducted.

16 HOW SUPPLIED/STORAGE AND HANDLING

Promethazine HCl and Codeine Phosphate Oral Solution is supplied as a clear, purple red, peach-mint flavor syrup containing promethazine HCl 6.25 mg/5 mL, codeine phosphate 10 mg/5 mL and alcohol 8% (v/v). It is available as follows:

Bottles of 16 fluid ounces (473 mL), NDC 0713-0823-75.

Keep bottles tightly closed.

Store at 20° to 25°C (68° to 77°F); excursions permitted from 15° to 30°C (59° to 86°F). [See USP Controlled Room Temperature.]

Protect from light.

Dispense in tight, light-resistant container (USP/NF) with a child-resistant closure.

Ensure that patients have an oral dosing dispenser that measures the appropriate volume in milliliters. Counsel patients on how to utilize an oral dosing dispenser and correctly measure the oral suspension as prescribed.

DEA Order Form Required.

17 PATIENT COUNSELING INFORMATION

Advise the patient to read the FDA-approved patient labeling (Medication Guide).

Addiction, Abuse, and Misuse
Inform patients that the use of Promethazine HCl and Codeine Phosphate Oral Solution, even when taken as recommended, can result in addiction, abuse, and misuse, which can lead to overdose and death [see Warnings and Precautions (5.1)]. Instruct patients not to share Promethazine HCl and Codeine Phosphate Oral Solution with others and to take steps to protect Promethazine HCl and Codeine Phosphate Oral Solution from theft or misuse.

Important Dosing and Administration Instructions
Instruct patients how to measure and take the correct dose of Promethazine HCl and Codeine Phosphate Oral Solution. Advise patients to measure Promethazine HCl and Codeine Phosphate Oral Solution with an accurate milliliter measuring device. Patients should be informed that a household teaspoon is not an accurate measuring device and could lead to overdosage. Advise patients to ask their pharmacist to recommend an appropriate measuring device and for instructions for measuring the correct dose [see Dosage and Administration (2.1), Warnings and Precautions (5.7)]. Advise patients not to increase the dose or dosing frequency of Promethazine HCl and Codeine Phosphate Oral Solution because serious adverse events such as respiratory depression may occur with overdosage [see Warnings and Precautions (5.2), Overdosage (10)].

Life-Threatening Respiratory Depression
Inform patients of the risk of life-threatening respiratory depression, including information that the risk is greatest when starting Promethazine HCl and Codeine Phosphate Oral Solution and that it can occur even at recommended dosages [see Warnings and Precautions (5.2)]. Advise patients how to recognize respiratory depression and to seek medical attention if breathing difficulties develop.

Accidental Ingestion
Inform patients that accidental ingestion, especially by children, may result in respiratory depression or death [see Warnings and Precautions (5.2)]. Instruct patients to take steps to store Promethazine HCl and Codeine Phosphate Oral Solution securely and to properly dispose of unused Promethazine HCl and Codeine Phosphate Oral Solution in accordance with the local state guidelines and/or regulations.

Ultra-Rapid Metabolism of Codeine and Other Risk Factors for Life-Threatening Respiratory Depression in Children
Advise caregivers that Promethazine HCl and Codeine Phosphate Oral Solution is not indicated for pediatric patients under 18 years of age, and is contraindicated in all children younger than 12 years of age and in children younger than 18 years of age following tonsillectomy and/or adenoidectomy.

Activities Requiring Mental Alertness
Advise patients to avoid engaging in hazardous tasks that require mental alertness and motor coordination such as operating machinery or driving a motor vehicle as Promethazine HCl and Codeine Phosphate Oral Solution may produce marked drowsiness [see Warnings and Precautions (5.8)].

Interactions with Benzodiazepines and Other Central Nervous System Depressants, Including Alcohol
Inform patients and caregivers that potentially fatal additive effects may occur if Promethazine HCl and Codeine Phosphate Oral Solution is used with benzodiazepines or other CNS depressants, including alcohol. Advise patients to avoid concomitant use of Promethazine HCl and Codeine Phosphate Oral Solution with benzodiazepines or other CNS depressants and to not use alcohol while taking Promethazine HCl and Codeine Phosphate Oral Solution [see Warnings and Precautions (5.10), Drug Interactions (7.4)].

Constipation
Advise patients of the potential for severe constipation [see Warnings and Precautions (5.11), Adverse Reactions (6)].

Anaphylaxis
Inform patients that anaphylaxis has been reported with ingredients contained in Promethazine HCl and Codeine Phosphate Oral Solution. Advise patients how to recognize such a reaction and when to seek medical attention [see Contraindications (4), Adverse Reactions (6)].

MAOI Interaction
Inform patients not to take Promethazine HCl and Codeine Phosphate Oral Solution while using or within 14 days of stopping any drugs that inhibit monoamine oxidase. Patients should not start MAOIs while taking Promethazine HCl and Codeine Phosphate Oral Solution [see Warnings and Precautions (5.16), Drug Interactions (7.6)].

Hypotension
Inform patients that Promethazine HCl and Codeine Phosphate Oral Solution may cause orthostatic hypotension and syncope. Instruct patients how to recognize symptoms of low blood pressure and how to reduce the risk of serious consequences should hypotension occur (e.g., sit or lie down, carefully rise from a sitting or lying position) [see Warnings and Precautions (5.18)].

Pregnancy
Advise patients that use of Promethazine HCl and Codeine Phosphate Oral Solution is not recommended during pregnancy [see Use in Specific Populations (8.1)].

Neonatal Opioid Withdrawal Syndrome
Inform female patients of reproductive potential that use of Promethazine HCl and Codeine Phosphate Oral Solution during pregnancy can result in neonatal opioid withdrawal syndrome, which may be life-threatening if not recognized and treated [see Warnings and Precautions (5.19), Use in Specific Populations (8.1)].

Embryo-Fetal Toxicity
Inform female patients of reproductive potential that Promethazine HCl and Codeine Phosphate Oral Solution can cause fetal harm and to inform their healthcare provider of a known or suspected pregnancy [see Use in Specific Populations (8.1)].

Lactation
Advise women that breastfeeding is not recommended during treatment with Promethazine HCl and Codeine Phosphate Oral Solution [see Use in Specific Populations (8.2)].

Infertility
Inform patients that chronic use of opioids, such as codeine, a component of Promethazine HCl and Codeine Phosphate Oral Solution, may cause reduced fertility. It is not known whether these effects on fertility are reversible [see Use in Specific Populations (8.3)].

Adrenal Insufficiency
Inform patients that Promethazine HCl and Codeine Phosphate Oral Solution could cause adrenal insufficiency, a potentially life-threatening condition. Adrenal insufficiency may present with non-specific symptoms and signs such as nausea, vomiting, anorexia, fatigue, weakness, dizziness, and low blood pressure. Advise patients to seek medical attention if they experience a constellation of these symptoms [see Warnings and Precautions (5.20)].

Serotonin Syndrome
Inform patients that Promethazine HCl and Codeine Phosphate Oral Solution could cause a rare but potentially life-threatening condition resulting from concomitant administration of serotonergic drugs. Warn patients of the symptoms of serotonin syndrome and to seek medical attention right away if symptoms develop. Instruct patients to inform their physicians if they are taking, or plan to take serotonergic medications. [see Adverse Reactions (6), Drug Interactions (7.5)].

Disposal of Unused Promethazine HCl and Codeine Phosphate Oral Solution
Advise patients to properly dispose of unused Promethazine HCl and Codeine Phosphate Oral Solution. Advise patients to throw the drug in the household trash following these steps. 1) Remove them from their original containers and mix them with an undesirable substance, such as used coffee grounds or kitty litter (this makes the drug less appealing to children and pets, and unrecognizable to people who may intentionally go through the trash seeking drugs). 2) Place the mixture in a sealable bag, empty can, or other container to prevent the drug from leaking or breaking out of a garbage bag, or to dispose of in accordance with local state guidelines and/or regulations.

Distributed by:
Cosette Pharmaceuticals NC Laboratories, LLC
Lincolnton, NC 28092

8-0779CP2

LB8860
Rev. 01
08/2025

MEDICATION GUIDE

Promethazine (proe METH a zeen)

Hydrochloride and Codeine (KOE deen) Phosphate Oral Solution, C-V

What is the most important information I should know about Promethazine Hydrochloride and Codeine Phosphate Oral Solution?

Promethazine Hydrochloride and Codeine Phosphate Oral Solution is not for children under 18 years of age.

Promethazine Hydrochloride and Codeine Phosphate Oral Solution can cause serious side effects, including:

- Addiction, abuse and misuse. Taking Promethazine Hydrochloride and Codeine Phosphate Oral Solution or other medicines that contain an opioid can cause addiction, abuse, and misuse, which can lead to overdose and death. This can happen even if you take Promethazine Hydrochloride and Codeine Phosphate Oral Solution exactly as prescribed by your healthcare provider. Your risk of addiction, abuse, and misuse is increased if you or a family member has a history of drug or alcohol abuse or addiction, or mental health problems.
  - Do not share your Promethazine Hydrochloride and Codeine Phosphate Oral Solution with other people.
  - Keep Promethazine Hydrochloride and Codeine Phosphate Oral Solution in a safe place away from children.
- Life-threatening breathing problems (respiratory depression). Promethazine Hydrochloride and Codeine Phosphate Oral Solution can cause breathing problems (respiratory depression) that can happen at any time during treatment and can lead to death. Your risk of breathing problems is greatest when you first start taking Promethazine Hydrochloride and Codeine Phosphate Oral Solution, are taking other medicines that can cause breathing problems, have certain lung problems, are elderly or have certain other health problems. Children are at higher risk for respiratory depression. Breathing problems can happen even if you take Promethazine Hydrochloride and Codeine Phosphate Oral Solution exactly as prescribed by your healthcare provider.

Call your healthcare provider or get emergency medical help right away if anyone taking Promethazine Hydrochloride and Codeine Phosphate Oral Solution, or your breastfeeding baby has any of the symptoms below:

- increased sleepiness
- confusion
- difficulty breathing
- shallow breathing
- limpness

Keep Promethazine Hydrochloride and Codeine Phosphate Oral Solution in a safe place away from children. Accidental use of even 1 dose of Promethazine Hydrochloride and Codeine Phosphate Oral Solution, especially by a child, is a medical emergency and can cause breathing problems (respiratory depression) which can lead to death. If a child accidentally takes Promethazine Hydrochloride and Codeine Phosphate Oral Solution, get emergency help right away.

- Overdose and death due to medicine dosing errors. Overdose and death can happen if you measure the wrong dose of Promethazine Hydrochloride and Codeine Phosphate Oral Solution. Always use an accurate milliliter (mL) measuring device to measure the correct amount of Promethazine Hydrochloride and Codeine Phosphate Oral Solution. Do not use a household teaspoon to measure your medicine. You may accidentally take too much. You can ask your pharmacist for the measuring device you should use and how to measure the correct dose.
- Breathing problems (respiratory depression)that can lead to death and opioid withdrawal can happen if you start taking or stop taking other medicines while taking Promethazine Hydrochloride and Codeine Phosphate Oral Solution, including:
  - certain antibiotics
  - certain medicines to treat a fungal infection
  - certain medicines to treat Human Immunodeficiency Virus (HIV)-1 infection, Acquired Immune Deficiency Syndrome (AIDS), or Hepatitis C
  - rifampin
  - carbamazepine
  - phenytoin
- Severe drowsiness, breathing problems (respiratory depression), coma, and death can happen in adults and children who take Promethazine Hydrochloride and Codeine Phosphate Oral Solution with benzodiazepines, or other central nervous system depressants, including alcohol.
  - Do not take any benzodiazepines or medicines that can cause drowsiness or sleepiness during treatment with Promethazine Hydrochloride and Codeine Phosphate Oral Solution. Ask your healthcare provider for a list of these medicines if you are not sure.
  - Do not drink alcohol during treatment with Promethazine Hydrochloride and Codeine Phosphate Oral Solution.
- Opioid withdrawal in a newborn. Use of Promethazine Hydrochloride and Codeine Phosphate Oral Solution during pregnancy can cause withdrawal symptoms in your newborn baby that could be life-threatening if not recognized and treated. You should not take Promethazine Hydrochloride and Codeine Phosphate Oral Solution if you are pregnant. Tell your healthcare provider right away if you are pregnant or think you may be pregnant.

What is Promethazine Hydrochloride and Codeine Phosphate Oral Solution?

- Promethazine Hydrochloride and Codeine Phosphate Oral Solution is a prescription medicine used in adults to temporarily treat cough and upper respiratory symptoms that you can have with allergies or a common cold. Promethazine Hydrochloride and Codeine Phosphate Oral Solution contains 2 medicines, promethazine and codeine. Promethazine is an antihistamine. Codeine is an opioid (narcotic) cough suppressant.
- Promethazine Hydrochloride and Codeine Phosphate Oral Solution is a federal controlled substance (C-V) because it contains codeine that can be abused or lead to dependence. Keep Promethazine Hydrochloride and Codeine Phosphate Oral Solution in a safe place to prevent misuse and abuse. Selling or giving away Promethazine Hydrochloride and Codeine Phosphate Oral Solution may harm others, and is against the law. Tell your healthcare provider if you have ever abused or been dependent on alcohol, prescription medicines or street drugs.

Who should not take Promethazine Hydrochloride and Codeine Phosphate Oral Solution?

Promethazine Hydrochloride and Codeine Phosphate Oral Solution is not for children under 18 years of age. See “What is the most important information I should know about Promethazine Hydrochloride and Codeine Phosphate Oral Solution?”

Do not take Promethazine Hydrochloride and Codeine Phosphate Oral Solution if you:

- have severe breathing problems (respiratory depression). See “What is the most important information I should know about Promethazine Hydrochloride and Codeine Phosphate Oral Solution?”
- have a blockage (obstruction) in your bowel such as a paralytic ileus.
- take a medicine called a monoamine oxidase inhibitor (MAOI).
  - Do not take an MAOI within 14 days after you stop taking Promethazine Hydrochloride and Codeine Phosphate Oral Solution.
  - Do not start taking Promethazine Hydrochloride and Codeine Phosphate Oral Solution if you stopped taking an MAOI in the last 14 days.
- have a type of glaucoma called “narrow angle glaucoma”.
- have problems with your urinary tract or difficulty urinating (urinary retention).
- are allergic to promethazine, codeine, or any of the ingredients in Promethazine Hydrochloride and Codeine Phosphate Oral Solution. See the end of this Medication Guide for a complete list of ingredients in Promethazine Hydrochloride and Codeine Phosphate Oral Solution. You may have an increased risk of an allergic reaction to Promethazine Hydrochloride and Codeine Phosphate Oral Solution if you are allergic to certain other opioid medicines.

Ask your healthcare provider if you have any questions about this information.

Before you take Promethazine Hydrochloride and Codeine Phosphate Oral Solution, tell your healthcare provider about all of your medical conditions, including if you:

- have a drug addiction
- have lung or breathing problems
- have a fever and are coughing up mucus
- have had a recent head injury
- have had brain tumor or other brain problems
- have or have had seizures
- have pain in your stomach-area (abdomen)
- have constipation or other bowel problems
- have bile duct or pancreas problems
- have kidney or liver problems
- have prostate problems
- have problems with your urinary tract or difficulty urinating
- have uncontrolled spasms of your face, neck or muscles of your body, arms and legs (dystonia)
- have a history of neuroleptic malignant syndrome (NMS)
- have blood disorders including low white blood cells
- have low blood pressure (hypotension)
- have adrenal gland problems
- plan to have surgery
- are pregnant or plan to become pregnant. Promethazine Hydrochloride and Codeine Phosphate Oral Solution can harm your unborn baby. See “What is the most important information I should know about Promethazine Hydrochloride and Codeine Phosphate Oral Solution?”
- are breastfeeding or plan to breastfeed. Codeine passes into your breast milk and can cause serious side effects in your baby including increased sleepiness, breathing problems (respiratory depression), and death. It is not known if promethazine can pass into your breast milk. You and your healthcare provider should decide if you will take Promethazine Hydrochloride and Codeine Phosphate Oral Solution or breastfeed. You should not do both. See “What should I avoid while taking Promethazine Hydrochloride and Codeine Phosphate Oral Solution?”
- plan to have children. Promethazine Hydrochloride and Codeine Phosphate Oral Solution may affect the ability to have a child in females and males (fertility problems). It is not known if these fertility problems will be reversible, even after you stop taking Promethazine Hydrochloride and Codeine Phosphate Oral Solution.

Tell your healthcare provider about all the medicines you take, including prescription and over-the-counter medicines, vitamins, and herbal supplements.

Taking Promethazine Hydrochloride and Codeine Phosphate Oral Solution with certain other medicines can cause side effects or affect how well Promethazine Hydrochloride and Codeine Phosphate Oral Solution or the other medicines work. Do not start or stop taking other medicines without talking to your healthcare provider.

Especially tell your healthcare provider if you:

- See “What is the most important information I should know about Promethazine Hydrochloride and Codeine Phosphate Oral Solution?”
- take pain medicines such as opioids (narcotics).
- take cold or allergy medicines that contain antihistamines or cough suppressants.
- drink alcohol.
- take muscle relaxants.
- take certain medicines used to treat mood, anxiety, psychotic or thought disorders, or depression, including monoamine oxidase inhibitors (MAOIs), tricyclics, selective serotonin reuptake inhibitors (SSRIs), selective serotonin-norepinephrine reuptake inhibitors (SNRIs), or antipsychotics.
- take water pills (diuretics).
- take medicines called “anticholinergics” used to treat asthma, chronic bronchitis (COPD), or stomach problems.

Ask your healthcare provider if you are not sure if you take one of these medicines.

How should I take Promethazine Hydrochloride and Codeine Phosphate Oral Solution?

- See “What is the most important information I should know about Promethazine Hydrochloride and Codeine Phosphate Oral Solution?”
- Take Promethazine Hydrochloride and Codeine Phosphate Oral Solution exactly as your healthcare provider tells you to take it. Do not change your dose without talking to your healthcare provider.
- Take Promethazine Hydrochloride and Codeine Phosphate Oral Solution by mouth only.
- Do not take more than 30 mL of Promethazine Hydrochloride and Codeine Phosphate Oral Solution in 24 hours.
- Take Promethazine Hydrochloride and Codeine Phosphate Oral Solution using an accurate milliliter (mL) measuring device. If you do not have one, ask your pharmacist to give you a measuring device to measure the correct amount of Promethazine Hydrochloride and Codeine Phosphate Oral Solution. Do not use a household teaspoon to measure your medicine. You may accidently take too much.
- Do not overfill the measuring device.
- Rinse your measuring device with water after each use.
- If you take too much Promethazine Hydrochloride and Codeine Phosphate Oral Solution, call your healthcare provider or go to the nearest hospital emergency room right away.
- Tell your healthcare provider if your cough does not get better within 5 days of treatment with Promethazine Hydrochloride and Codeine Phosphate Oral Solution.

What should I avoid while taking Promethazine Hydrochloride and Codeine Phosphate Oral Solution?

- Avoid driving a car or operating machinery during treatment with Promethazine Hydrochloride and Codeine Phosphate Oral Solution. Promethazine Hydrochloride and Codeine Phosphate Oral Solution can cause you to be drowsy, slow your thinking and motor skills, and affect your vision.
- Do not drink alcohol during treatment with Promethazine Hydrochloride and Codeine Phosphate Oral Solution. Drinking alcohol with Promethazine Hydrochloride and Codeine Phosphate Oral Solution can increase your chances of having serious side effects, accidental overdose, and cause death.

Avoid the use of Promethazine Hydrochloride and Codeine Phosphate Oral Solution if you:

- are pregnant. Use of Promethazine Hydrochloride and Codeine Phosphate Oral Solution during pregnancy can cause withdrawal symptoms in your newborn baby that could be life-threatening if not recognized and treated. Tell your healthcare provider right away if you are pregnant or think you may be pregnant.
- are breastfeeding. Use of Promethazine Hydrochloride and Codeine Phosphate Oral Solution while breastfeeding can cause severe breathing problems (respiratory depression) in your breastfed infant that could be life-threatening.

What are the possible side effects of Promethazine Hydrochloride and Codeine Phosphate Oral Solution?

Promethazine Hydrochloride and Codeine Phosphate Oral Solution may cause serious side effects, including:

- See “What is the most important information I should know about Promethazine Hydrochloride and Codeine Phosphate Oral Solution?”
- Bowel problems including severe constipation or stomach pain. See “Who should not take Promethazine Hydrochloride and Codeine Phosphate Oral Solution?”
- Increased pressure in your head (increased intracranial pressure). Avoid the use of Promethazine Hydrochloride and Codeine Phosphate Oral Solution if you have a head injury or have been told that you have changes in the tissue of your brain (brain lesions) or increased pressure in your head.
- Neuroleptic malignant syndrome (NMS) which can lead to death. Tell your healthcare provider right away if you have any of the following symptoms of NMS:
-
  - high fever
  - stiff muscles
  - confusion
  - sweating
  - changes in pulse, heart rate, or blood pressure

- Uncontrolled spasms of your face and neck muscles, or muscles of your body, arms, and legs (dystonia). These muscle spasms can cause abnormal movements and body positions, and speech problems. These spasms may happen after one dose of Promethazine Hydrochloride and Codeine Phosphate Oral Solution. Tell your healthcare provider if you have any of these symptoms.
- Increased risk of seizures in people with seizure disorders. If you have a seizure disorder, Promethazine Hydrochloride and Codeine Phosphate Oral Solution may increase how often you have seizures.

- Low blood pressure. A sudden drop in blood pressure can happen in some people during treatment with Promethazine Hydrochloride and Codeine Phosphate Oral Solution and this may cause you to feel dizzy, faint, lightheaded, or weak, especially when you stand up (orthostatic hypotension). Your risk of having this problem may be increased if you take Promethazine Hydrochloride and Codeine Phosphate Oral Solution with certain other medicines that lower blood pressure. If you have any of these symptoms while taking Promethazine Hydrochloride and Codeine Phosphate Oral Solution, sit or lie down. Do not change your body position too fast. Get up slowly from sitting or lying down.
- Adrenal gland problems. Promethazine Hydrochloride and Codeine Phosphate Oral Solution can cause serious and life-threatening adrenal gland problems. Your healthcare provider may do blood tests to check for adrenal gland problems. Call your healthcare provider right away if you have any of these symptoms:
-
  - nausea
  - vomiting
  - not wanting to eat (anorexia)
  - fatigue
  - weakness
  - dizziness
  - low blood pressure

- Changes in laboratory blood levels, including high blood sugar and false pregnancy test reading.

The most common side effects of Promethazine Hydrochloride and Codeine Phosphate Oral Solution include:

- sleepiness
- confusion
- coordination problems
- decrease in mental and physical performance
- lack of energy
- lightheadedness
- dizziness
- headache
- irritability
- anxiety
- restlessness
- nervousness
- tremor
- dry mouth
- difficulty urinating
- sweating
- shortness of breath
- nausea
- vomiting
- constipation

These are not all the possible side effects of Promethazine Hydrochloride and Codeine Phosphate Oral Solution.

Call your doctor for medical advice about side effects. You may report side effects to FDA at 1-800-FDA-1088.

How should I store Promethazine Hydrochloride and Codeine Phosphate Oral Solution?

- Store Promethazine Hydrochloride and Codeine Phosphate Oral Solution at room temperature between 68°F to 77°F (20°C to 25°C).
- Store Promethazine Hydrochloride and Codeine Phosphate Oral Solution in a tightly closed container, in a dry, cool place away from heat or direct sunlight.
- Keep Promethazine Hydrochloride and Codeine Phosphate Oral Solution and all medicines out of the reach of children.

How should I dispose of Promethazine Hydrochloride and Codeine Phosphate Oral Solution?

Remove unused Promethazine Hydrochloride and Codeine Phosphate Oral Solution from the container and mix it with an undesirable, non-toxic substance such as cat litter or used coffee grounds to make it less appealing to children and pets. Place the mixture in a container such as a sealed plastic bag and throw it away in the household trash. You can also follow your state or local guidelines on how to safely throw away Promethazine Hydrochloride and Codeine Phosphate Oral Solution.

General information about the safe and effective use of Promethazine Hydrochloride and Codeine Phosphate Oral Solution.

Medicines are sometimes prescribed for purposes other than those listed in a Medication Guide. Do not use Promethazine Hydrochloride and Codeine Phosphate Oral Solution for a condition for which it was not prescribed. Do not give Promethazine Hydrochloride and Codeine Phosphate Oral Solution to other people, even if they have the same symptoms that you have. It may harm them.

You can ask your pharmacist or healthcare provider for information about Promethazine Hydrochloride and Codeine Phosphate Oral Solution that is written for health professionals.

What are the ingredients in Promethazine Hydrochloride and Codeine Phosphate Oral Solution?

Active ingredients: promethazine hydrochloride and codeine phosphate

Inactive ingredients: anhydrous citric acid, ascorbic acid, D&C Red # 33, edetate disodium, FD&C Blue #1, methylparaben, peach-mint flavor, propylene glycol, propylparaben, purified water, saccharin sodium, sodium benzoate, sodium citrate anhydrous, sodium metabisulfite, sucrose.

Distributed by: Cosette Pharmaceuticals NC Laboratories, LLC
Lincolnton, NC 28092

For more information, call 1-800-922-1038.

This Medication Guide has been approved by the U.S. Food and Drug Administration. Revised:08/2025

PRINCIPAL DISPLAY PANEL

NDC 0713-0823-75

Rx only

Promethazine Hydrochloride and Codeine Phosphate Oral Solution CV

6.25 mg and 10 mg per 5 mL

Alcohol 8% (v/v)

WARNINGS: Contains sodium metabisulfite, a sulfite that may cause allergic-type reactions.

PHARMACIST: Dispense the accompanying Medication Guide to each patient.

16 fl. oz. (473 mL)